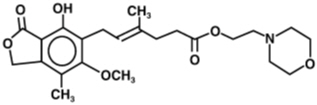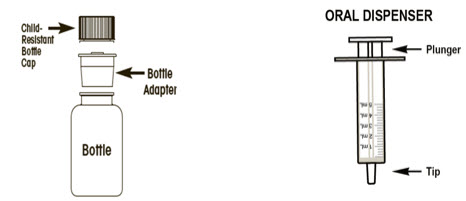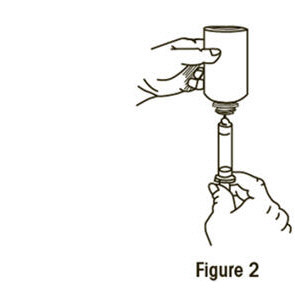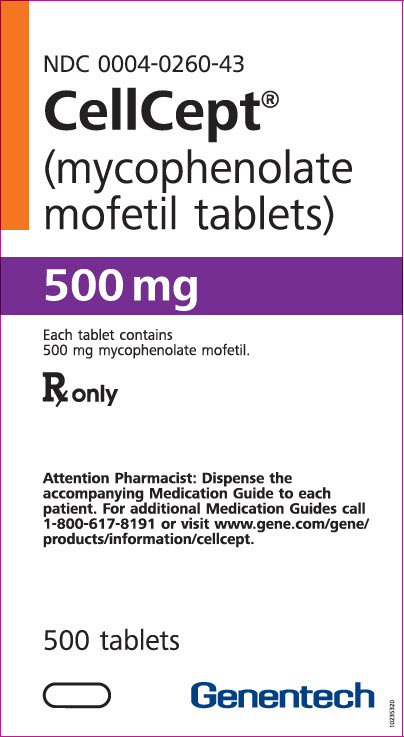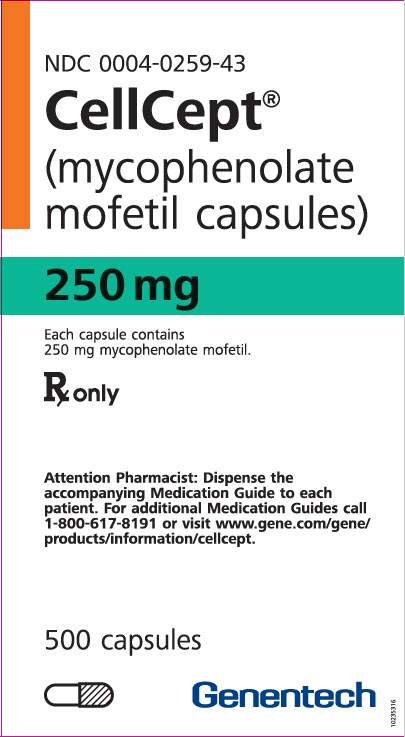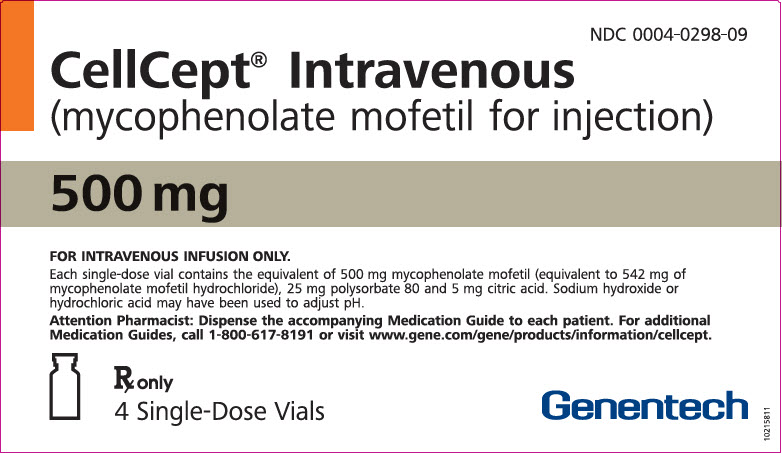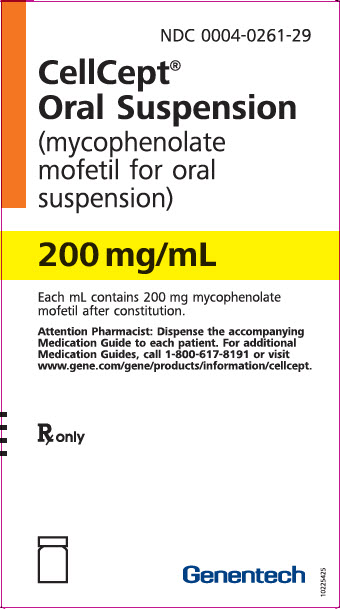 DRUG LABEL: CellCept
NDC: 0004-0260 | Form: TABLET, FILM COATED
Manufacturer: Genentech, Inc.
Category: prescription | Type: HUMAN PRESCRIPTION DRUG LABEL
Date: 20251125

ACTIVE INGREDIENTS: MYCOPHENOLATE MOFETIL 500 mg/1 1
INACTIVE INGREDIENTS: MICROCRYSTALLINE CELLULOSE; POVIDONE K90; CROSCARMELLOSE SODIUM; MAGNESIUM STEARATE; HYPROMELLOSE, UNSPECIFIED; HYDROXYPROPYL CELLULOSE, UNSPECIFIED; TITANIUM DIOXIDE; POLYETHYLENE GLYCOL 400; FERROSOFERRIC OXIDE; FD&C BLUE NO. 2; FERRIC OXIDE RED; TALC; AMMONIA; SHELLAC

HIGHLIGHTS OF PRESCRIBING INFORMATION

These highlights do not include all the information needed to use CELLCEPT® safely and effectively. See full prescribing information for CELLCEPT®
CELLCEPT® (mycophenolate mofetil) capsules, for oral use
CELLCEPT® (mycophenolate mofetil) tablets, for oral use
CELLCEPT® Oral Suspension (mycophenolate mofetil), for oral suspension
CELLCEPT® Intravenous (mycophenolate mofetil) for injection, for intravenous use
Initial U.S. Approval: 1995

WARNING: EMBRYOFETAL TOXICITY, MALIGNANCIES and SERIOUS INFECTIONS

See full prescribing information for complete boxed warning

- Use during pregnancy is associated with increased risks of first trimester pregnancy loss and congenital malformations. Avoid if safer treatment options are available. Females of reproductive potential must be counseled regarding pregnancy prevention and planning [see Warnings and Precautions (5.1)].
- Increased risk of development of lymphoma and other malignancies, particularly of the skin [see Warnings and Precautions (5.2)].
- Increased susceptibility to infections, including opportunistic infections and severe infections with fatal outcomes [see Warnings and Precautions (5.3)].

RECENT MAJOR CHANGES

Warnings and Precautions (5.8) | 05/2025

1 INDICATIONS AND USAGE

CELLCEPT is an antimetabolite immunosuppressant indicated for the prophylaxis of organ rejection in adult and pediatric recipients 3 months of age and older of allogeneic kidney, heart or liver transplants, in combination with other immunosuppressants. (1)

2 DOSAGE AND ADMINISTRATION

ADULTS | DOSAGE
Kidney Transplant | 1 g twice daily, orally or intravenously (IV) over no less than 2 h (2.2)
Heart Transplant | 1.5 g twice daily orally or IV, over no less than 2 h (2.3)
Liver Transplant | 1.5 g twice daily orally or 1g twice daily IV over no less than 2 h (2.4)
PEDIATRICS
Kidney Transplant | 600 mg/m^2 orally twice daily, up to maximum of 2 g daily (2.2)
Heart Transplant | 600 mg/m^2 orally twice daily (starting dose) up to a maximum of 900 mg/m^2 twice daily (3 g or 15 mL of oral suspension) (2.3)
Liver Transplant | 600 mg/m^2 orally twice daily (starting dose) up to a maximum of 900 mg/m^2 twice daily (3 g or 15 mL of oral suspension) (2.4)

- CELLCEPT Intravenous is an alternative when patients cannot tolerate oral medication. Administer within 24 hours following transplantation, until patients can tolerate oral medication, up to 14 days. (2.1)
- Reduce or interrupt dosing in the event of neutropenia. (2.5)
- See full prescribing information (FPI) for: adjustments for renal impairment and neutropenia (2.5), preparation of oral suspension and IV solution. (2.6)

3 DOSAGE FORMS AND STRENGTHS

- Capsules: 250 mg
- Tablets: 500 mg
- For Oral Suspension: 35 g mycophenolate mofetil, powder for reconstitution (200 mg/mL upon reconstitution)
- For Injection: 500 mg mycophenolate mofetil in a single-dose vial for reconstitution.

4 CONTRAINDICATIONS

- History of hypersensitivity, including anaphylaxis, to mycophenolate mofetil, mycophenolic acid or any component of the drug product (4)
- Patients allergic to Polysorbate 80 (present in CELLCEPT IV) (4)

5 WARNINGS AND PRECAUTIONS

- Blood Dyscrasias (Neutropenia, Red Blood Cell Aplasia): Monitor with blood tests; consider treatment interruption or dose reduction. (5.4)
- Gastrointestinal Complications: Monitor for complications such as bleeding, ulceration and perforations, particularly in patients with underlying gastrointestinal disorders. (5.5)
- Hypoxanthine-Guanine Phosphoribosyl-Transferase Deficiency: Avoid use of CELLCEPT. (5.6)
- Acute Inflammatory Syndrome Associated with Mycophenolate Products: Monitor for this paradoxical inflammatory reaction. (5.7)
- Hypersensitivity Reactions: Discontinue CELLCEPT; treat and monitor until signs and symptoms resolve. (5.8)
- Immunizations: Avoid live attenuated vaccines. (5.9)
- Local Reactions with Rapid Intravenous Administration: CELLCEPT Intravenous must not be administered by rapid or bolus intravenous injection. (5.10)
- Phenylketonurics: Oral suspension contains aspartame. (5.11)
- Blood Donation: Avoid during therapy and for 6 weeks thereafter. (5.12)
- Semen Donation: Avoid during therapy and for 90 days thereafter. (5.13)
- Potential Impairment on Driving and Use of Machinery: CELLCEPT may affect ability to drive or operate machinery. (5.15)

6 ADVERSE REACTIONS

The most common adverse reactions in clinical trials (20 % or greater) include diarrhea, leukopenia, infection, vomiting, and there is evidence of a higher frequency of certain types of infections e.g., opportunistic infection. (6.1)

To report SUSPECTED ADVERSE REACTIONS, contact Genentech at 1-888-835-2555 or FDA at 1-800-FDA-1088 or www.fda.gov/medwatch.com

7 DRUG INTERACTIONS

- See FPI for drugs that may interfere with systemic exposure and reduce CELLCEPT efficacy: antacids with magnesium or aluminum hydroxide, proton pump inhibitors, drugs that interfere with enterohepatic recirculation, telmisartan, calcium-free phosphate binders. (7.1)
- CELLCEPT may reduce effectiveness of oral contraceptives. Use of additional barrier contraceptive methods is recommended. (7.2)
- See FPI for other important drug interactions. (7)

8 USE IN SPECIFIC POPULATIONS

- Male Patients: Sexually active male patients and/or their female partners are recommended to use effective contraception during treatment of the male patient and for at least 90 days after cessation of treatment (8.3)

FULL PRESCRIBING INFORMATION

WARNING: EMBRYOFETAL TOXICITY, MALIGNANCIES and SERIOUS INFECTIONS

- Use during pregnancy is associated with increased risks of first trimester pregnancy loss and congenital malformations. Avoid if safer treatment options are available. Females of reproductive potential must be counseled regarding pregnancy prevention and planning [see Warnings and Precautions (5.1), Use in Special Populations (8.1, 8.3)].
- Increased risk of development of lymphoma and other malignancies, particularly of the skin [see Warnings and Precautions (5.2)].
- Increased susceptibility to bacterial, viral, fungal and protozoal infections, including opportunistic infections and viral reactivation of hepatitis B and C, which may lead to hospitalizations and fatal outcomes [see Warnings and Precautions (5.3)].

1 INDICATIONS AND USAGE

CELLCEPT [mycophenolate mofetil (MMF)] is indicated for the prophylaxis of organ rejection, in adult and pediatric recipients 3 months of age and older of allogeneic kidney [see Clinical Studies (14.1)], heart [see Clinical Studies (14.2)] or liver transplants [see Clinical Studies (14.3)], in combination with other immunosuppressants.

2 DOSAGE AND ADMINISTRATION

2.1 Important Administration Instructions

CELLCEPT should not be used without the supervision of a physician with experience in immunosuppressive therapy.

CELLCEPT Capsules, Tablets and Oral Suspension

CELLCEPT oral dosage forms (capsules, tablets or oral suspension) should not be used interchangeably with mycophenolic acid delayed-release tablets without supervision of a physician with experience in immunosuppressive therapy because the rates of absorption following the administration of CELLCEPT oral dosage forms and mycophenolic acid delayed-release tablets are not equivalent.

CELLCEPT tablets should not be crushed and CELLCEPT capsules should not be opened or crushed. Patients should avoid inhalation or contact of the skin or mucous membranes with the powder contained in CELLCEPT capsules and oral suspension. If such contact occurs, they must wash the area of contact thoroughly with soap and water. In case of ocular contact, rinse eyes with plain water.

The initial oral dose of CELLCEPT should be given as soon as possible following kidney, heart or liver transplant. It is recommended that CELLCEPT be administered on an empty stomach. In stable transplant patients, however, CELLCEPT may be administered with food if necessary [see Clinical Pharmacology (12.3)]. Once reconstituted, CELLCEPT Oral Suspension must not be mixed with any liquids prior to dose administration. If needed, CELLCEPT Oral Suspension can be administered via a nasogastric tube with a minimum size of 8 French (minimum 1.7 mm interior diameter).

Patients should be instructed to take a missed dose as soon as they remember, except if it is closer than 2 hours to the next scheduled dose; in this case, they should continue to take CELLCEPT at the usual times.

CELLCEPT Intravenous

CELLCEPT Intravenous is recommended for patients unable to take oral CELLCEPT. CELLCEPT Intravenous should be administered within 24 hours following transplant. CELLCEPT Intravenous can be administered for up to 14 days; however, patients should be switched to oral CELLCEPT as soon as they can tolerate oral medication.

CELLCEPT Intravenous must be reconstituted before use [see Dosage and Administration (2.6)]. CELLCEPT Intravenous is incompatible with other intravenous infusion solutions and should not be mixed or administered concurrently via the same infusion catheter with other intravenous drugs or infusion admixtures.

CELLCEPT Intravenous must not be administered as a bolus. Following reconstitution, CELLCEPT Intravenous must be administered by slow intravenous infusion over a period of no less than 2 hours by either peripheral or central vein, as rapid infusion increases the risk of local adverse reactions such as phlebitis and thrombosis [see Adverse Reactions (6.1)].

2.2 Dosage Recommendations for Kidney Transplant Patients

Adults

The recommended dosage for adult kidney transplant patients is 1 g orally or intravenously infused over no less than 2 hours, twice daily (total daily dose of 2 g).

Pediatrics (3 months and older)

Pediatric dosing is based on body surface area (BSA). The recommended dosage of CELLCEPT oral suspension for pediatric kidney transplant patients 3 months and older is 600 mg/m^2, administered twice daily (maximum total daily dose of 2 g or 10 mL of the oral suspension). Pediatric patients with BSA ≥ 1.25 m^2 may be dosed with capsules or tablets as follows:

Table 1 Pediatric Kidney Transplant: Dosage Using Capsules or Tablets
Body Surface Area | Dosage
1.25 m^2 to <1.5 m^2 | CELLCEPT capsule 750 mg twice daily (1.5 g total daily dose)
≥ 1.5 m^2 | CELLCEPT capsules or tablets 1 g twice daily (2 g total daily dose)

2.3 Dosage Recommendations for Heart Transplant Patients

Adults

The recommended dosage of CELLCEPT for adult heart transplant patients is 1.5 g orally or intravenously infused over no less than 2 hours administered twice daily (total daily dose of 3 g).

Pediatrics (3 months and older)

The recommended starting dosage of CELLCEPT oral suspension for pediatric heart transplant patients 3 months and older is 600 mg/m^2, administered twice daily. If well tolerated, the dose can be increased to a maintenance dosage of 900 mg/m^2 twice daily (maximum total daily dose of 3 g or 15 mL of the oral suspension). The dose may be individualized based on clinical assessment.

Pediatric patients with BSA ≥1.25 m^2 may be started on therapy with capsules or tablets as follows:

Table 2 Pediatric Heart Transplant: Pediatric Starting Dosage Using Capsules or Tablets
Body Surface Area | Starting Dosage [Maximum maintenance dose: 3 g total daily.]
1.25 m^2 to <1.5 m^2 | CELLCEPT capsule 750 mg twice daily (1.5 g total daily dose)
≥ 1.5 m^2 | CELLCEPT capsules or tablets 1 g twice daily (2 g total daily dose)

2.4 Dosage Recommendations for Liver Transplant Patients

Adults

The recommended dosage of CELLCEPT for adult liver transplant patients is 1.5 g administered orally twice daily (total daily dose of 3 g) or 1 g infused intravenously over no less than 2 hours, twice daily (total daily dose of 2 g).

Pediatrics (3 months and older)

The recommended starting dosage of CELLCEPT oral suspension for pediatric liver transplant patients 3 months of age and older is 600 mg/m^2, administered twice daily. If well tolerated, the dose can be increased to a maintenance dosage of 900 mg/m^2 twice daily (maximum total daily dose of 3 g or 15 mL of the oral suspension). The dose may be individualized based on clinical assessment.

Pediatric patients with BSA ≥1.25 m^2 may be started on therapy with capsules or tablets as follows:

Table 3 Pediatric Liver Transplant: Pediatric Starting Dosage Using Capsules or Tablets
Body Surface Area | Starting Dosage [Maximum maintenance dose: 3 g total daily.]
1.25 m^2 to <1.5 m^2 | CELLCEPT capsule 750 mg twice daily (1.5 g total daily dose)
≥ 1.5 m^2 | CELLCEPT capsules or tablets 1 g twice daily (2 g total daily dose)

2.5 Dosage Modifications: Patients with Renal Impairment, Neutropenia

Renal Impairment

No dosage modifications are needed in kidney transplant patients with delayed graft function postoperatively [see Clinical Pharmacology (12.3)]. In kidney transplant patients with severe chronic impairment of the graft (GFR <25 mL/min/1.73 m^2), do not administer doses of CELLCEPT greater than 1 g twice a day. These patients should be carefully monitored [see Clinical Pharmacology (12.3)].

Neutropenia

If neutropenia develops (ANC <1.3 × 10^3/µL), dosing with CELLCEPT should be interrupted or reduced, appropriate diagnostic tests performed, and the patient managed appropriately [see Warnings and Precautions (5.4) and Adverse Reactions (6.1)].

2.6 Preparation Instructions of Oral Suspension and Intravenous for Pharmacists

General Preparation Instructions Before Handling the Formulations

Mycophenolate mofetil (MMF) has demonstrated teratogenic effects in humans. Follow applicable special handling and disposal procedures^1 [see Warnings and Precautions (5.1), Adverse Reactions (6.2), Use in Specific Populations (8.1, 8.3), How Supplied/Storage and Handling (16.1)].

Care should be taken to avoid inhalation or direct contact with skin or mucous membranes of the dry powder or the constituted suspension because MMF has demonstrated teratogenic effects in humans. Wearing disposable gloves is recommended during reconstitution and when wiping the outer surface of the bottle/cap and the table surface after reconstitution. If such contact occurs, wash hands thoroughly with soap and water; rinse eyes with water.

Alert patients that they and others should also avoid inhalation or contact of the skin or mucous membranes with the oral suspension. Advise them to wash the area thoroughly with soap and water if such contact occurs; if ocular contact occurs, rinse eyes with plain water.

CELLCEPT Oral Suspension

CELLCEPT Oral Suspension must be reconstituted by the pharmacist prior to dispensing to the patient. CELLCEPT Oral Suspension should not be mixed with any other medication. After reconstitution, the oral suspension contains 200 mg/mL MMF.

Before proceeding with the reconstitution steps read the general preparation instructions above [see General Preparation Instructions Before Handling the Formulations]. The following are the steps for reconstitution:

1. Tap the closed bottle several times to loosen the powder.
2. Measure 94 mL of water in a graduated cylinder.
3. Add approximately half the total amount of water for reconstitution to the bottle and shake the closed bottle well for about 1 minute.
4. Add the remainder of water and shake the closed bottle well for about 1 minute.
5. Remove the child-resistant cap and push bottle adapter into neck of bottle.
6. Close bottle with child-resistant cap tightly. This will assure the proper seating of the bottle adapter in the bottle and child-resistant status of the cap.
7. Write the date of expiration of the constituted suspension on the bottle label. (The shelf-life of the constituted suspension is 60 days.)
8. Dispense with the "Instruction for Use" and oral dispensers. Alert patients to read the important handling information described in the instructions for use.

Store reconstituted suspension at 25°C (77°F); excursions permitted to 15°C to 30°C (59°F to 86°F). Storage in a refrigerator at 2°C to 8°C (36°F to 46°F) is acceptable. Do not freeze. Discard any unused portion 60 days after constitution.

CELLCEPT Intravenous

Before proceeding with the preparation steps for CELLCEPT Intravenous read the general preparation instructions [see General Preparation Instructions Before Handling the Formulations] and note the following:

- CELLCEPT Intravenous does not contain an antibacterial preservative; therefore, reconstitution and dilution of the product must be performed under aseptic conditions.
- This product is sealed under vacuum and should retain a vacuum throughout its shelf life. If a lack of vacuum in the vial is noted while adding the diluent, the vial should not be used.

CELLCEPT Intravenous must be reconstituted and further diluted. A detailed description of the preparation is given below.

Table 4 Preparation Instructions of CELLCEPT Intravenous for Pharmacists
Preparation of the 1g dose | 1. Reconstitute two (2) vials of CELLCEPT Intravenous by injecting 14 mL of 5% Dextrose Injection USP into each vial. 2. Gently shake the vial to dissolve the drug. 3. Inspect the resulting slightly yellow solution for particulate matter and discoloration prior to further dilution. Discard the vials if particulate matter or discoloration is observed. 4. Dilute the contents of the two reconstituted vials (approximately 2 × 15 mL) into 140 mL of 5% Dextrose Injection USP. 5. Inspect the resulting infusion solution and discard if particulate matter or discoloration is observed.
Preparation of the 1.5 g dose | 1. Reconstitute three (3) vials of CELLCEPT Intravenous by injecting 14 mL of 5% Dextrose Injection USP into each vial. 2. Gently shake the vial to dissolve the drug. 3. Inspect the resulting slightly yellow solution for particulate matter and discoloration prior to further dilution. Discard the vials if particulate matter or discoloration is observed. 4. Dilute the contents of the three reconstituted vials (approximately 3 × 15 mL) into 210 mL of 5% Dextrose Injection USP. 5. Inspect the resulting infusion solution and discard if particulate matter or discoloration is observed.

The administration of the infusion should be initiated within 4 hours of reconstitution and dilution of the drug product. Keep solutions at 25°C (77°F); excursions permitted to 15°C to 30°C (59°F to 86°F). Discard unused portion of the reconstituted solutions.

CELLCEPT Injection should not be mixed or administered concurrently via the same infusion catheter with other intravenous drugs or infusion admixtures.

3 DOSAGE FORMS AND STRENGTHS

CELLCEPT is available in the following dosage forms and strengths:

Capsules | 250 mg mycophenolate mofetil, two-piece hard gelatin capsules, blue-brown, "CELLCEPT 250" printed in black on the blue cap and "Roche" on the brown body
Tablets | 500 mg mycophenolate mofetil, lavender-colored, caplet-shaped, film-coated tablets engraved with "CELLCEPT 500" on one side and "Roche" on the other
For oral suspension | 35 g mycophenolate mofetil white to off-white powder for reconstitution (200 mg/mL upon reconstitution)
For injection | 500 mg mycophenolate mofetil white to off-white lyophilized powder, in a single-dose vial for reconstitution

4 CONTRAINDICATIONS

CELLCEPT is contraindicated in patients with a history of hypersensitivity, including anaphylaxis, to mycophenolate mofetil (MMF), mycophenolic acid (MPA) or any component of the drug product [see Warnings and Precautions (5.8)]. CELLCEPT Intravenous is contraindicated in patients who are allergic to Polysorbate 80 (TWEEN).

5 WARNINGS AND PRECAUTIONS

5.1 Embryofetal Toxicity

Use of MMF during pregnancy is associated with an increased risk of first trimester pregnancy loss and an increased risk of congenital malformations, especially external ear and other facial abnormalities including cleft lip and palate, and anomalies of the distal limbs, heart, esophagus, kidney and nervous system. Females of reproductive potential must be made aware of these risks and must be counseled regarding pregnancy prevention and planning. Avoid use of MMF during pregnancy if safer treatment options are available [see Use in Specific Populations (8.1, 8.3)].

5.2 Lymphoma and Other Malignancies

Patients receiving immunosuppressants, including CELLCEPT, are at increased risk of developing lymphomas and other malignancies, particularly of the skin [see Adverse Reactions (6.1)]. The risk appears to be related to the intensity and duration of immunosuppression rather than to the use of any specific agent. For patients with increased risk for skin cancer, exposure to sunlight and UV light should be limited by wearing protective clothing and using a broad-spectrum sunscreen with a high protection factor.

Post-transplant lymphoproliferative disorder (PTLD) developed in 0.4% to 1% of patients receiving CELLCEPT (2 g or 3 g) with other immunosuppressive agents in controlled clinical trials of kidney, heart and liver transplant patients [see Adverse Reactions (6.1)]. The majority of PTLD cases appear to be related to Epstein Barr Virus (EBV) infection. The risk of PTLD appears greatest in those individuals who are EBV seronegative, a population which includes many young children. In pediatric patients, no other malignancies besides PTLD were observed in clinical trials [see Adverse Reactions (6.1)].

5.3 Serious Infections

Patients receiving immunosuppressants, including CELLCEPT, are at increased risk of developing bacterial, fungal, protozoal and new or reactivated viral infections, including opportunistic infections. The risk increases with the total immunosuppressive load. These infections may lead to serious outcomes, including hospitalizations and death [see Adverse Reactions (6.1, 6.2)].

Serious viral infections reported include:

- Polyomavirus-associated nephropathy (PVAN), especially due to BK virus infection
- JC virus-associated progressive multifocal leukoencephalopathy (PML), and
- Cytomegalovirus (CMV) infections: CMV seronegative transplant patients who receive an organ from a CMV seropositive donor are at highest risk of CMV viremia and CMV disease.
- Viral reactivation in patients infected with Hepatitis B and C
- COVID-19

Consider dose reduction or discontinuation of CELLCEPT in patients who develop new infections or reactivate viral infections, weighing the risk that reduced immunosuppression represents to the functioning allograft.

PVAN, especially due to BK virus infection, is associated with serious outcomes, including deteriorating renal function and renal graft loss [see Adverse Reactions (6.2)]. Patient monitoring may help detect patients at risk for PVAN.

PML, which is sometimes fatal, commonly presents with hemiparesis, apathy, confusion, cognitive deficiencies, and ataxia [see Adverse Reactions (6.2)]. In immunosuppressed patients, physicians should consider PML in the differential diagnosis in patients reporting neurological symptoms.

The risk of CMV viremia and CMV disease is highest among transplant recipients seronegative for CMV at time of transplant who receive a graft from a CMV seropositive donor. Therapeutic approaches to limiting CMV disease exist and should be routinely provided. Patient monitoring may help detect patients at risk for CMV disease.

Viral reactivation has been reported in patients infected with HBV or HCV. Monitoring infected patients for clinical and laboratory signs of active HBV or HCV infection is recommended.

5.4 Blood Dyscrasias: Neutropenia and Pure Red Cell Aplasia (PRCA)

Severe neutropenia [absolute neutrophil count (ANC) <0.5 × 10^3/µL] developed in transplant patients receiving CELLCEPT 3 g daily [see Adverse Reactions (6.1)]. Patients receiving CELLCEPT should be monitored for neutropenia. Neutropenia has been observed most frequently in the period from 31 to 180 days post-transplant in patients treated for prevention of kidney, heart and liver rejection. The development of neutropenia may be related to CELLCEPT itself, concomitant medications, viral infections, or a combination of these causes. If neutropenia develops (ANC <1.3 × 10^3/µL), dosing with CELLCEPT should be interrupted or the dose reduced, appropriate diagnostic tests performed, and the patient managed appropriately [see Dosage and Administration (2.5)].

Patients receiving CELLCEPT should be instructed to report immediately any evidence of infection, unexpected bruising, bleeding or any other manifestation of bone marrow depression.

Consider monitoring with complete blood counts weekly for the first month, twice monthly for the second and third months, and monthly for the remainder of the first year.

Cases of pure red cell aplasia (PRCA) have been reported in patients treated with CELLCEPT in combination with other immunosuppressive agents. In some cases, PRCA was found to be reversible with dose reduction or cessation of CELLCEPT therapy. In transplant patients, however, reduced immunosuppression may place the graft at risk.

5.5 Gastrointestinal Complications

Gastrointestinal bleeding requiring hospitalization, ulceration and perforations were observed in clinical trials. Physicians should be aware of these serious adverse effects particularly when administering CELLCEPT to patients with a gastrointestinal disease.

5.6 Patients with Hypoxanthine-Guanine Phosphoribosyl-Transferase Deficiency (HGPRT)

CELLCEPT is an inosine monophosphate dehydrogenase (IMPDH) inhibitor; therefore it should be avoided in patients with hereditary deficiencies of hypoxanthine-guanine phosphoribosyl-transferase (HGPRT) such as Lesch-Nyhan and Kelley-Seegmiller syndromes because it may cause an exacerbation of disease symptoms characterized by the overproduction and accumulation of uric acid leading to symptoms associated with gout such as acute arthritis, tophi, nephrolithiasis or urolithiasis and renal disease including renal failure.

5.7 Acute Inflammatory Syndrome Associated with Mycophenolate Products

Acute inflammatory syndrome (AIS) has been reported with the use of MMF and mycophenolate products, and some cases have resulted in hospitalization. AIS is a paradoxical pro-inflammatory reaction characterized by fever, arthralgias, arthritis, muscle pain and elevated inflammatory markers including, C-reactive protein and erythrocyte sedimentation rate, without evidence of infection or underlying disease recurrence. Symptoms occur within weeks to months of initiation of treatment or a dose increase. After discontinuation, improvement of symptoms and inflammatory markers are usually observed within 24 to 48 hours.

Monitor patients for symptoms and laboratory parameters of AIS when starting treatment with mycophenolate products or when increasing the dosage. Discontinue treatment and consider other treatment alternatives based on the risk and benefit for the patient.

5.8 Hypersensitivity Reactions

Postmarketing cases of hypersensitivity reactions, including angioedema and anaphylaxis, have been reported with CELLCEPT. These reactions generally occurred within hours to the next day after initiating CELLCEPT. If signs or symptoms of hypersensitivity reaction occur, discontinue CELLCEPT; treat and monitor until symptoms resolve [see Contraindications (4)].

5.9 Immunizations

During treatment with CELLCEPT, the use of live attenuated vaccines should be avoided (e.g., intranasal influenza, measles, mumps, rubella, oral polio, BCG, yellow fever, varicella, and TY21a typhoid vaccines) and patients should be advised that vaccinations may be less effective. Advise patients to discuss with the physician before seeking any immunizations.

5.10 Local Reactions with Rapid Intravenous Administration

CELLCEPT Intravenous solution must not be administered by rapid or bolus intravenous injection as rapid infusion increases the risk of local adverse reactions such as phlebitis and thrombosis [see Adverse Reactions (6.1)].

5.11 Risks in Patients with Phenylketonuria

Phenylalanine can be harmful to patients with phenylketonuria (PKU). CELLCEPT Oral Suspension contains aspartame, a source of phenylalanine (0.56 mg phenylalanine/mL suspension). Before prescribing CELLCEPT Oral Suspension to a patient with PKU, consider the combined daily amount of phenylalanine from all sources, including CELLCEPT.

5.12 Blood Donation

Patients should not donate blood during therapy and for at least 6 weeks following discontinuation of CELLCEPT because their blood or blood products might be administered to a female of reproductive potential or a pregnant woman.

5.13 Semen Donation

Based on animal data, men should not donate semen during therapy and for 90 days following discontinuation of CELLCEPT [see Use In Specific Populations (8.3)].

5.14 Effect of Concomitant Medications on Mycophenolic Acid Concentrations

A variety of drugs have potential to alter systemic MPA exposure when co-administered with CELLCEPT. Therefore, determination of MPA concentrations in plasma before and after making any changes to immunosuppressive therapy, or when adding or discontinuing concomitant medications, may be appropriate to ensure MPA concentrations remain stable.

5.15 Potential Impairment of Ability to Drive or Operate Machinery

CELLCEPT may impact the ability to drive and use machines. Patients should avoid driving or using machines if they experience somnolence, confusion, dizziness, tremor, or hypotension during treatment with CELLCEPT [see Adverse Reactions (6.1)].

6 ADVERSE REACTIONS

The following adverse reactions are discussed in greater detail in other sections of the label:

- Embryofetal Toxicity [see Warnings and Precautions (5.1)]
- Lymphomas and Other Malignancies [see Warnings and Precautions 5.2)]
- Serious Infections [see Warnings and Precautions (5.3)]
- Blood Dyscrasias: Neutropenia, Pure Red Cell Aplasia [see Warnings and Precautions (5.4)]
- Gastrointestinal Complications [see Warnings and Precautions (5.5)]
- Acute Inflammatory Syndrome Associated with Mycophenolate Products [see Warnings and Precautions (5.7)]
- Hypersensitivity Reactions [see Warnings and Precautions (5.8)]

6.1 Clinical Trials Experience

Because clinical trials are conducted under widely varying conditions, adverse reaction rates observed in the clinical trials of a drug cannot be directly compared to rates in the clinical trials of another drug and may not reflect the rates observed in practice.

An estimated total of 1557 adult patients received CELLCEPT during pivotal clinical trials in the prevention of acute organ rejection. Of these, 991 were included in the three renal studies, 277 were included in one hepatic study, and 289 were included in one cardiac study. Patients in all study arms also received cyclosporine and corticosteroids.

The data described below primarily derive from five randomized, active-controlled double-blind 12-month trials of CELLCEPT in de novo kidney (3) heart (1) and liver (1) transplant patients [see Clinical Studies (14.1, 14.2, and 14.3)].

CELLCEPT Oral

The incidence of adverse reactions for CELLCEPT was determined in five randomized, comparative, double-blind trials in the prevention of rejection in kidney, heart and liver transplant patients (two active- and one placebo-controlled trials, one active-controlled trial, and one active-controlled trial, respectively) [see Clinical Studies (14.1, 14.2 and 14.3)].

The three de novo kidney studies with 12-month duration compared two dose levels of oral CELLCEPT (1 g twice daily and 1.5 g twice daily) with azathioprine (2 studies) or placebo (1 study) when administered in combination with cyclosporine (Sandimmune®) and corticosteroids to prevent acute rejection episodes. One study also included anti-thymocyte globulin (ATGAM®) induction therapy.

In the de novo heart transplantation study with 12-month duration, patients received CELLCEPT 1.5 g twice daily (n=289) or azathioprine 1.5 to 3 mg/kg/day (n=289), in combination with cyclosporine (Sandimmune® or Neoral®) and corticosteroids as maintenance immunosuppressive therapy.

In the de novo liver transplantation study with 12-month duration, patients received CELLCEPT 1 g twice daily intravenously for up to 14 days followed by CELLCEPT 1.5 g twice daily orally or azathioprine 1 to 2 mg/kg/day intravenously followed by azathioprine 1 to 2 mg/kg/day orally, in combination with cyclosporine (Neoral®) and corticosteroids as maintenance immunosuppressive therapy. The total number of patients enrolled was 565.

Approximately 53% of the kidney transplant patients, 65% of the heart transplant patients, and 48% of the liver transplant patients were treated for more than 1 year. Adverse reactions reported in ≥ 20% of patients in the CELLCEPT treatment groups are presented below. The safety data of three kidney transplantation studies are pooled together.

Table 5 Adverse Reactions in Controlled Studies of De Novo Kidney, Heart or Liver Transplantation Reported in ≥20% of Patients in the CELLCEPT Group
Adverse drug reaction | Kidney Studies |  |  | Heart Study |  | Liver Study
Adverse drug reaction | CellCept 2g/day (n=501) or 3g/day (n=490) | AZA 1 to 2 mg/kg/day or 100 to 150 mg/day | Placebo | CellCept 3g/day | AZA 1.5 to 3 mg/kg/day | CellCept 3g/day | AZA 1 to 2 mg/kg/day
 | (n=991) | (n=326) | (n=166) | (n=289) | (n=289) | (n=277) | (n=287)
System Organ Class | % | % | % | % | % | % | %
Infections and infestations
Bacterial infections | 39.9 | 33.7 | 37.3 | - | - | 27.4 | 26.5
Viral infections | - ["-" Indicates that the incidence was below the cutoff value of 20% for inclusion in the table.] | - | - | 31.1 | 24.9 | - | -
Blood and lymphatic system disorders
Anemia | 20.0 | 23.6 | 2.4 | 45.0 | 47.1 | 43.0 | 53.0
Ecchymosis | - | - | - | 20.1 | 9.7 | - | -
Leukocytosis | - | - | - | 42.6 | 37.4 | 22.4 | 21.3
Leukopenia | 28.6 | 24.8 | 4.2 | 34.3 | 43.3 | 45.8 | 39.0
Thrombocytopenia | - | - | - | 24.2 | 28.0 | 38.3 | 42.2
Metabolism and nutrition disorders
Hypercholesterolemia | - | - | - | 46.0 | 43.9 | - | -
Hyperglycemia | - | - | - | 48.4 | 53.3 | 43.7 | 48.8
Hyperkalemia | - | - | - | - | - | 22.0 | 23.7
Hypocalcemia | - | - | - | - | - | 30.0 | 30.0
Hypokalemia | - | - | - | 32.5 | 26.3 | 37.2 | 41.1
Hypomagnesemia | - | - | - | 20.1 | 14.2 | 39.0 | 37.6
Psychiatric disorders
Depression | - | - | - | 20.1 | 15.2 | - | -
Insomnia | - | - | - | 43.3 | 39.8 | 52.3 | 47.0
Nervous system disorders
Dizziness | - | - | - | 34.3 | 33.9 | - | -
Headache | - | - | - | 58.5 | 55.4 | 53.8 | 49.1
Tremor | - | - | - | 26.3 | 25.6 | 33.9 | 35.5
Cardiac disorders
Tachycardia | - | - | - | 22.8 | 21.8 | 22.0 | 15.7
Vascular disorders
Hypertension | 27.5 | 32.2 | 19.3 | 78.9 | 74.0 | 62.1 | 59.6
Hypotension | - | - | - | 34.3 | 40.1 | - | -
Respiratory, thoracic and mediastinal disorders
Cough | - | - | - | 40.5 | 32.2 | - | -
Dyspnea | - | - | - | 44.3 | 44.3 | 31.0 | 30.3
Pleural effusion | - | - | - | - | - | 34.3 | 35.9
Gastrointestinal disorders
Abdominal pain | 22.4 | 23.0 | 11.4 | 41.9 | 39.4 | 62.5 | 51.2
Constipation | - | - | - | 43.6 | 38.8 | 37.9 | 38.3
Decreased appetite | - | - | - | - | - | 25.3 | 17.1
Diarrhea | 30.4 | 20.9 | 13.9 | 52.6 | 39.4 | 51.3 | 49.8
Dyspepsia | - | - | - | 22.1 | 22.1 | 22.4 | 20.9
Nausea | - | - | - | 56.1 | 60.2 | 54.5 | 51.2
Vomiting | - | - | - | 39.1 | 34.6 | 32.9 | 33.4
Hepatobiliary disorders
Blood lactate dehydrogenase increased | - | - | - | 23.5 | 18.3 | - | -
Hepatic enzyme increased | - | - | - | - | - | 24.9 | 19.2
Skin and subcutaneous tissues disorders
Rash | - | - | - | 26.0 | 20.8 | - | -
Renal and urinary disorders
Blood creatinine increased | - | - | - | 42.2 | 39.8 | - | -
Blood urea increased | - | - | - | 36.7 | 34.3 | - | -
General disorders and administration site conditions
Asthenia | - | - | - | 49.1 | 41.2 | 35.4 | 33.8
Edema ["Edema" includes peripheral edema, facial edema, scrotal edema.] | 21.0 | 28.2 | 8.4 | 67.5 | 55.7 | 48.4 | 47.7
Pain ["Pain" includes musculoskeletal pain (myalgia, neck pain, back pain).] | 24.8 | 32.2 | 9.6 | 79.2 | 77.5 | 74.0 | 77.5
Pyrexia | - | - | - | 56.4 | 53.6 | 52.3 | 56.1

In the three de novo kidney studies, patients receiving 2 g/day of CELLCEPT had an overall better safety profile than did patients receiving 3 g/day of CELLCEPT.

Post-transplant lymphoproliferative disease (PTLD, pseudolymphoma) developed in 0.4% to 1% of patients receiving CELLCEPT (2 g or 3 g daily) with other immunosuppressive agents in controlled clinical trials of kidney, heart and liver transplant patients followed for at least 1 year [see Warnings and Precautions (5.2)]. Non-melanoma skin carcinomas occurred in 1.6% to 4.2% of patients, other types of malignancy in 0.7% to 2.1% of patients. Three-year safety data in kidney and heart transplant patients did not reveal any unexpected changes in incidence of malignancy compared to the 1-year data. In pediatric patients, PTLD was observed in 1.35% (2/148) by 12 months post-transplant.

Cytopenias, including leukopenia, anemia, thrombocytopenia and pancytopenia are a known risk associated with mycophenolate and may lead or contribute to the occurrence of infections and hemorrhages [see Warnings and Precautions (5.3)]. Severe neutropenia (ANC <0.5 × 10^3/µL) developed in up to 2% of kidney transplant patients, up to 2.8% of heart transplant patients and up to 3.6% of liver transplant patients receiving CELLCEPT 3 g daily [see Warnings and Precautions (5.4) and Dosage and Administration (2.5)].

The most common opportunistic infections in patients receiving CELLCEPT with other immunosuppressants were mucocutaneous candida, CMV viremia/syndrome, and herpes simplex. The proportion of patients with CMV viremia/syndrome was 13.5%. In patients receiving CELLCEPT (2 g or 3 g) in controlled studies for prevention of kidney, heart or liver rejection, fatal infection/sepsis occurred in approximately 2% of kidney and heart patients and in 5% of liver patients [see Warnings and Precautions (5.3)].

The most serious gastrointestinal disorders reported were ulceration and hemorrhage, which are known risks associated with CELLCEPT. Mouth, esophageal, gastric, duodenal, and intestinal ulcers often complicated by hemorrhage, as well as hematemesis, melena, and hemorrhagic forms of gastritis and colitis were commonly reported during the pivotal clinical trials, while the most common gastrointestinal disorders were diarrhea, nausea and vomiting. Endoscopic investigation of patients with CELLCEPT-related diarrhea revealed isolated cases of intestinal villous atrophy [see Warnings and Precautions (5.5)].

The following adverse reactions were reported with 3% to <20% incidence in kidney, heart, and liver transplant patients treated with CELLCEPT, in combination with cyclosporine and corticosteroids.

Table 6 Adverse Reactions in Controlled Studies of De Novo Kidney, Heart or Liver Transplantation Reported in 3% to <20% of Patients Treated with CELLCEPT in Combination with Cyclosporine and Corticosteroids
System Organ Class | Adverse Reactions
Body as a Whole | cellulitis, chills, hernia, malaise
Infections and Infestations | fungal infections
Hematologic and Lymphatic | coagulation disorder, ecchymosis, pancytopenia
Urogenital | hematuria
Cardiovascular | hypotension
Metabolic and Nutritional | acidosis, alkaline phosphatase increased, hyperlipemia, hypophosphatemia, weight loss
Digestive | esophagitis, flatulence, gastritis, gastrointestinal hemorrhage, hepatitis, ileus, nausea and vomiting, stomach ulcer, stomatitis
Neoplasm benign, malignant and unspecified | neoplasm
Skin and Appendages | skin benign neoplasm, skin carcinoma
Psychiatric | confusional state
Nervous | hypertonia, paresthesia, somnolence
Musculoskeletal | arthralgia, myasthenia

Pediatrics

The type and frequency of adverse events in a clinical study for prevention of kidney allograft rejection in 100 pediatric patients 3 months to 18 years of age dosed with CELLCEPT oral suspension 600 mg/m^2 twice daily (up to 1 g twice daily) were generally similar to those observed in adult patients dosed with CELLCEPT capsules at a dose of 1 g twice daily with the exception of abdominal pain, fever, infection, pain, sepsis, diarrhea, vomiting, pharyngitis, respiratory tract infection, hypertension, leukopenia, and anemia, which were observed in a higher proportion in pediatric patients.

Safety information in pediatric heart transplant or pediatric liver transplant patients treated with CELLCEPT is supported by an open-label study in pediatric liver transplant patients and publications; the type and frequency of the reported adverse reactions are consistent with those observed in pediatric patients following renal transplant and in adults.

Geriatrics

Geriatric patients (≥65 years), particularly those who are receiving CELLCEPT as part of a combination immunosuppressive regimen, may be at increased risk of certain infections (including cytomegalovirus [CMV] tissue invasive disease) and possibly gastrointestinal hemorrhage and pulmonary edema, compared to younger individuals [see Warnings and Precautions (5.3) and Adverse Reactions (6.1)].

CELLCEPT Intravenous

The safety profile of CELLCEPT Intravenous was determined from a single, double-blind, controlled comparative study of the safety of 2 g/day of intravenous and oral CELLCEPT in kidney transplant patients in the immediate post-transplant period (administered for the first 5 days). The potential venous irritation of CELLCEPT Intravenous was evaluated by comparing the adverse reactions attributable to peripheral venous infusion of CELLCEPT Intravenous with those observed in the intravenous placebo group; patients in the placebo group received active medication by the oral route.

Adverse reactions attributable to peripheral venous infusion were phlebitis and thrombosis, both observed at 4% in patients treated with CELLCEPT Intravenous.

6.2 Postmarketing Experience

The following adverse reactions have been identified during post-approval use of CELLCEPT. Because these reactions are reported voluntarily from a population of uncertain size, it is not always possible to reliably estimate their frequency or establish a causal relationship to drug exposure:

- Embryo-Fetal Toxicity: Congenital malformations and spontaneous abortions, mainly in the first trimester, have been reported following exposure to mycophenolate mofetil (MMF) in combination with other immunosuppressants during pregnancy [see Warnings and Precautions (5.1), and Use in Specific Populations (8.1), (8.3)]. Congenital malformations include:
  - Facial malformations: cleft lip, cleft palate, micrognathia, hypertelorism of the orbits
  - Abnormalities of the ear and eye: abnormally formed or absent external/middle ear, coloboma, microphthalmos
  - Malformations of the fingers: polydactyly, syndactyly, brachydactyly
  - Cardiac abnormalities: atrial and ventricular septal defects
  - Esophageal malformations: esophageal atresia
  - Nervous system malformations: such as spina bifida.
- Cardiovascular: Venous thrombosis has been reported in patients treated with CELLCEPT administered intravenously.
- Digestive: Colitis, pancreatitis
- Hematologic and Lymphatic: Bone marrow failure, cases of pure red cell aplasia (PRCA) and hypogammaglobulinemia have been reported in patients treated with CELLCEPT in combination with other immunosuppressive agents [see Warnings and Precautions (5.4)].
- Immune: Hypersensitivity reactions, including anaphylaxis and angioedema [see Warnings and Precautions (5.8)], hypogammaglobinemia.
- Infections: Meningitis, infectious endocarditis, tuberculosis, atypical mycobacterial infection, progressive multifocal leukoencephalopathy, BK virus infection, viral reactivation of hepatitis B and hepatitis C, protozoal infections [see Warnings and Precautions (5.3)].
- Respiratory: Bronchiectasis, interstitial lung disease, fatal pulmonary fibrosis, have been reported rarely and should be considered in the differential diagnosis of pulmonary symptoms ranging from dyspnea to respiratory failure in post-transplant patients receiving CELLCEPT.
- Vascular: Lymphocele

7 DRUG INTERACTIONS

7.1 Effect of Other Drugs on CELLCEPT

Table 7 Drug Interactions with CELLCEPT that Affect Mycophenolic Acid (MPA) Exposure
Antacids with Magnesium or Aluminum Hydroxide
Clinical Impact | Concomitant use with an antacid containing magnesium or aluminum hydroxide decreases MPA systemic exposure [see Clinical Pharmacology (12.3)], which may reduce CELLCEPT efficacy.
Prevention or Management | Administer magnesium or aluminum hydroxide containing antacids at least 2h after CELLCEPT administration.
Proton Pump Inhibitors (PPIs)
Clinical Impact | Concomitant use with PPIs decreases MPA systemic exposure [see Clinical Pharmacology (12.3)], which may reduce CELLCEPT efficacy.
Prevention or Management | Monitor patients for alterations in efficacy when PPIs are co-administered with CELLCEPT.
Examples | Lansoprazole, pantoprazole
Drugs that Interfere with Enterohepatic Recirculation
Clinical Impact | Concomitant use with drugs that directly interfere with enterohepatic recirculation, or indirectly interfere with enterohepatic recirculation by altering the gastrointestinal flora, can decrease MPA systemic exposure [see Clinical Pharmacology (12.3)], which may reduce CELLCEPT efficacy.
Prevention or Management | Monitor patients for alterations in efficacy or CELLCEPT related adverse reactions when these drugs are co-administered with CELLCEPT.
Examples | Cyclosporine A, trimethoprim/sulfamethoxazole, bile acid sequestrants (cholestyramine), rifampin as well as aminoglycoside, cephalosporin, fluoroquinolone and penicillin classes of antimicrobials
Drugs Modulating Glucuronidation
Clinical Impact | Concomitant use with drugs inducing glucuronidation decreases MPA systemic exposure, potentially reducing CELLCEPT efficacy, while use with drugs inhibiting glucuronidation increases MPA systemic exposure [see Clinical Pharmacology (12.3)], which may increase the risk of CELLCEPT related adverse reactions.
Prevention or Management | Monitor patients for alterations in efficacy or CELLCEPT related adverse reactions when these drugs are co-administered with CELLCEPT.
Examples | Telmisartan (induces glucuronidation); isavuconazole (inhibits glucuronidation).
Calcium Free Phosphate Binders
Clinical Impact | Concomitant use with calcium free phosphate binders decrease MPA systemic exposure [see Clinical Pharmacology (12.3)], which may reduce CELLCEPT efficacy.
Prevention or Management | Administer calcium free phosphate binders at least 2 hours after CELLCEPT.
Examples | Sevelamer

7.2 Effect of CELLCEPT on Other Drugs

Table 8 Drug Interactions with CELLCEPT that Affect Other Drugs
Drugs that Undergo Renal Tubular Secretion
Clinical Impact | When concomitantly used with CELLCEPT, its metabolite MPAG, may compete with drugs eliminated by renal tubular secretion which may increase plasma concentrations and/or adverse reactions associated with these drugs.
Prevention or Management | Monitor for drug-related adverse reactions in patients with renal impairment.
Examples | Acyclovir, ganciclovir, probenecid, valacyclovir, valganciclovir
Combination Oral Contraceptives
Clinical Impact | Concomitant use with CELLCEPT decreased the systemic exposure to levonorgestrel, but did not affect the systemic exposure to ethinylestradiol [see Clinical Pharmacology (12.3)], which may result in reduced combination oral contraceptive effectiveness.
Prevention or Management | Use additional barrier contraceptive methods.

8 USE IN SPECIFIC POPULATIONS

8.1 Pregnancy

Pregnancy Exposure Registry

There is a pregnancy exposure registry that monitors pregnancy outcomes in women exposed to mycophenolate during pregnancy and those becoming pregnant within 6 weeks of discontinuing CELLCEPT treatment. To report a pregnancy or obtain information about the registry, visit www.mycophenolateREMS.com or call 1-800-617-8191.

Risk Summary

Use of mycophenolate mofetil (MMF) during pregnancy is associated with an increased risk of first trimester pregnancy loss and an increased risk of multiple congenital malformations in multiple organ systems [see Human Data]. Oral administration of mycophenolate to rats and rabbits during the period of organogenesis produced congenital malformations and pregnancy loss at doses less than the recommended clinical dose (0.01 to 0.05 times the recommended clinical doses in kidney and heart transplant patients) [see Animal Data].

Consider alternative immunosuppressants with less potential for embryofetal toxicity. Risks and benefits of CELLCEPT should be discussed with the pregnant woman.

The estimated background risk of pregnancy loss and congenital malformations in organ transplant populations is not clear. In the U.S. general population, the estimated background risk of major birth defects and miscarriage in clinically recognized pregnancies is 2 to 4% and 15 to 20%, respectively.

Data

Human Data

A spectrum of congenital malformations (including multiple malformations in individual newborns) has been reported in 23 to 27% of live births in MMF exposed pregnancies, based on published data from pregnancy registries. Malformations that have been documented include external ear, eye, and other facial abnormalities including cleft lip and palate, and anomalies of the distal limbs, heart, esophagus, kidney, and nervous system.

Based on published data from pregnancy registries, the risk of first trimester pregnancy loss has been reported at 45 to 49% following MMF exposure.

Animal Data

In animal reproductive toxicology studies, there were increased rates of fetal resorptions and malformations in the absence of maternal toxicity. Oral administration of MMF to pregnant rats from Gestational Day 7 to Day 16 produced increased embryofetal lethality and fetal malformations including anophthalmia, agnathia, and hydrocephaly at doses equivalent to 0.015 and 0.01 times the recommended human doses for renal and cardiac transplant patients, respectively, when corrected for BSA. Oral administration of MMF to pregnant rabbits from Gestational Day 7 to Day 19 produced increased embryofetal lethality and fetal malformations included ectopia cordis, ectopic kidneys, diaphragmatic hernia, and umbilical hernia at dose equivalents as low as 0.05 and 0.03 times the recommended human doses for renal and cardiac transplant patients, respectively, when corrected for BSA.

8.2 Lactation

Risk Summary

There are no data on the presence of mycophenolate in human milk, or the effects on milk production. There are limited data in the National Transplantation Pregnancy Registry on the effects of mycophenolate on a breastfed child [see Data]. Studies in rats treated with MMF have shown mycophenolic acid (MPA) to be present in milk. Because available data are limited, it is not possible to exclude potential risks to a breastfeeding infant.

The developmental and health benefits of breastfeeding should be considered along with the mother's clinical need for CELLCEPT and any potential adverse effects on the breastfed infant from CELLCEPT or from the underlying maternal condition.

Data

Limited information is available from the National Transplantation Pregnancy Registry. Of seven infants reported by the National Transplantation Pregnancy Registry to have been breastfed while the mother was taking mycophenolate, all were born at 34-40 weeks gestation, and breastfed for up to 14 months. No adverse events were reported.

8.3 Females and Males of Reproductive Potential

Females of reproductive potential must be made aware of the increased risk of first trimester pregnancy loss and congenital malformations and must be counseled regarding pregnancy prevention and planning.

Pregnancy Planning

For patients who are considering pregnancy, consider alternative immunosuppressants with less potential for embryofetal toxicity whenever possible. Risks and benefits of CELLCEPT should be discussed with the patient.

Pregnancy Testing

To prevent unplanned exposure during pregnancy, all females of reproductive potential should have a serum or urine pregnancy test with a sensitivity of at least 25 mIU/mL immediately before starting CELLCEPT. Another pregnancy test with the same sensitivity should be done 8 to 10 days later. Repeat pregnancy tests should be performed during routine follow-up visits. Results of all pregnancy tests should be discussed with the patient. In the event of a positive pregnancy test, consider alternative immunosuppressants with less potential for embryofetal toxicity whenever possible.

Contraception

Female Patients

Females of reproductive potential taking CELLCEPT must receive contraceptive counseling and use acceptable contraception (see Table 9 for acceptable contraception methods). Patients must use acceptable birth control during the entire CELLCEPT therapy, and for 6 weeks after stopping CELLCEPT, unless the patient chooses abstinence.

Patients should be aware that CELLCEPT reduces blood levels of the hormones from the oral contraceptive pill and could theoretically reduce its effectiveness [see Drug Interactions (7.2)].

Table 9 Acceptable Contraception Methods for Females of Reproductive Potential
Pick from the following birth control options:
Option 1
Methods to Use Alone | - Intrauterine devices (IUDs) - Tubal sterilization - Patient's partner vasectomy
OR
Option 2 | Hormone Methods choose 1 |  | Barrier Methods choose 1
Choose One Hormone Method AND One Barrier Method | Estrogen and Progesterone; - Oral Contraceptive Pill - Transdermal patch - Vaginal ring; Progesterone-only; - Injection - Implant | AND | - Diaphragm with spermicide - Cervical cap with spermicide - Contraceptive sponge - Male condom - Female condom
OR
Option 3 | Barrier Methods choose 1 |  | Barrier Methods choose 1
Choose One Barrier Method from each column (must choose two methods) | - Diaphragm with spermicide - Cervical cap with spermicide - Contraceptive sponge | AND | - Male condom - Female condom

Male Patients

Genotoxic effects have been observed in animal studies at exposures exceeding the human therapeutic exposures by approximately 1.25 times. Thus, the risk of genotoxic effects on sperm cells cannot be excluded. Based on this potential risk, sexually active male patients and/or their female partners are recommended to use effective contraception during treatment of the male patient and for at least 90 days after cessation of treatment. Also, based on the potential risk of genotoxic effects, male patients should not donate sperm during treatment with CELLCEPT and for at least 90 days after cessation of treatment [see Use in Special Populations (8.1), Nonclinical Toxicology (13.1), Patient Counseling Information (17.9)].

8.4 Pediatric Use

Safety and effectiveness have been established in pediatric patients 3 months and older for the prophylaxis of organ rejection of allogenic kidney, heart or liver transplants.

Kidney Transplant

Use of CELLCEPT in this population is supported by evidence from adequate and well-controlled studies of CELLCEPT in adults with additional data from one open-label, pharmacokinetic and safety study of CELLCEPT in pediatric patients after receiving allogeneic kidney transplant (100 patients, 3 months to 18 years of age) [see Dosage and Administration (2.2), Adverse Reactions (6.1), Clinical Pharmacology (12.3), Clinical Studies (14.1)].

Heart Transplant and Liver Transplant

Use of CELLCEPT in pediatric heart transplant and liver transplant patients is supported by adequate and well-controlled studies and pharmacokinetic data in adult heart transplant and liver transplant patients. Additional supportive data include pharmacokinetic data in pediatric kidney transplant and pediatric liver transplant patients (8 liver transplant patients, 9 months to 5 years of age, in an open-label, pharmacokinetic and safety study) and published evidence of clinical efficacy and safety in pediatric heart transplant and pediatric liver transplant patients [see Dosage and Administration (2.3, 2.4), Adverse Reactions (6.1), Clinical Pharmacology (12.3), Clinical Studies (14.1)].

8.5 Geriatric Use

Clinical studies of CELLCEPT did not include sufficient numbers of subjects aged 65 and over to determine whether they respond differently from younger subjects. Other reported clinical experience has not identified differences in responses between geriatric and younger patients. In general, dose selection for a geriatric patient should take into consideration the presence of decreased hepatic, renal or cardiac function and of concomitant drug therapies [see Adverse Reactions (6.1), Drug Interactions (7)].

8.6 Patients with Renal Impairment

Patients with Kidney Transplant

No dosage adjustments are needed in kidney transplant patients experiencing delayed graft function postoperatively but patients should be carefully monitored [see Clinical Pharmacology (12.3)]. In kidney transplant patients with severe chronic impairment of the graft (GFR <25 mL/min/1.73 m^2), no dose adjustments are necessary; however, doses greater than 1 g administered twice a day should be avoided.

Patients with Heart and Liver Transplant

No data are available for heart or liver transplant patients with severe chronic renal impairment. CELLCEPT may be used for heart or liver transplant patients with severe chronic renal impairment if the potential benefits outweigh the potential risks.

8.7 Patients with Hepatic Impairment

Patients with Kidney Transplant

No dosage adjustments are recommended for kidney transplant patients with severe hepatic parenchymal disease. However, it is not known whether dosage adjustments are needed for hepatic disease with other etiologies [see Clinical Pharmacology (12.3)].

Patients with Heart Transplant

No data are available for heart transplant patients with severe hepatic parenchymal disease.

10 OVERDOSAGE

Possible signs and symptoms of acute overdose include hematological abnormalities such as leukopenia and neutropenia, and gastrointestinal symptoms such as abdominal pain, diarrhea, nausea, vomiting, and dyspepsia.

The experience with overdose of CELLCEPT in humans is limited. The reported effects associated with overdose fall within the known safety profile of the drug. The highest dose administered to kidney transplant patients in clinical trials has been 4 g/day. In limited experience with heart and liver transplant patients in clinical trials, the highest doses used were 4 g/day or 5 g/day. At doses of 4 g/day or 5 g/day, there appears to be a higher rate, compared to the use of 3 g/day or less, of gastrointestinal intolerance (nausea, vomiting, and/or diarrhea), and occasional hematologic abnormalities, particularly neutropenia [see Warnings and Precautions (5.4)].

Treatment and Management

MPA and the phenolic glucuronide metabolite of MPA (MPAG) are usually not removed by hemodialysis. However, at high MPAG plasma concentrations (>100 µg/mL), small amounts of MPAG are removed. By increasing excretion of the drug, MPA can be removed by bile acid sequestrants, such as cholestyramine [see Clinical Pharmacology (12.3)].

11 DESCRIPTION

CELLCEPT (mycophenolate mofetil) is an antimetabolite immunosuppressant. It is the 2-morpholinoethyl ester of mycophenolic acid (MPA), an immunosuppressive agent; inosine monophosphate dehydrogenase (IMPDH) inhibitor.

The chemical name for mycophenolate mofetil (MMF) is 2-morpholinoethyl (E)-6-(1,3-dihydro-4-hydroxy-6-methoxy-7-methyl-3-oxo-5-isobenzofuranyl)-4-methyl-4-hexenoate. It has an empirical formula of C23H31NO7, a molecular weight of 433.50, and the following structural formula:

MMF is a white to off-white crystalline powder. It is slightly soluble in water (43 µg/mL at pH 7.4); the solubility increases in acidic medium (4.27 mg/mL at pH 3.6). It is freely soluble in acetone, soluble in methanol, and sparingly soluble in ethanol. The apparent partition coefficient in 1-octanol/water (pH 7.4) buffer solution is 238. The pKa values for MMF are 5.6 for the morpholino group and 8.5 for the phenolic group.

MMF hydrochloride has a solubility of 65.8 mg/mL in 5% Dextrose Injection USP (D5W). The pH of the reconstituted solution is 2.4 to 4.1.

CELLCEPT is available for oral administration as capsules containing 250 mg of MMF, tablets containing 500 mg of MMF, and as a powder for oral suspension which, when reconstituted, contains 200 mg/mL of MMF.

Inactive ingredients in CELLCEPT 250 mg capsules include croscarmellose sodium, magnesium stearate, povidone (K-90) and pregelatinized starch. The capsule shells contain black iron oxide, FD&C blue #2, gelatin, red iron oxide, silicon dioxide, sodium lauryl sulfate, titanium dioxide, and yellow iron oxide.

Inactive ingredients in CELLCEPT 500 mg tablets include croscarmellose sodium, magnesium stearate, microcrystalline cellulose, povidone (K-90), and Opadry® lavender Y-5R-10272-A (hydroxypropyl methylcellulose, hydroxypropyl cellulose, titanium dioxide, polyethylene glycol 400, FD&C Blue No. 2 aluminum lake [indigo carmine aluminum lake], and red iron oxide).

Inactive ingredients in CELLCEPT Oral Suspension include aspartame, citric acid anhydrous, colloidal silicon dioxide, methylparaben, mixed fruit flavor, sodium citrate dihydrate, sorbitol, soybean lecithin, and xanthan gum.

CELLCEPT Intravenous is the hydrochloride salt of MMF. The chemical name for the hydrochloride salt of MMF is 2-morpholinoethyl (E)-6-(1,3-dihydro-4-hydroxy-6-methoxy-7-methyl-3-oxo-5-isobenzofuranyl)-4-methyl-4-hexenoate hydrochloride. It has an empirical formula of C23H31NO7 HCl and a molecular weight of 469.96.

CELLCEPT Intravenous is available as a sterile white to off-white lyophilized powder in single-dose vials containing MMF hydrochloride for administration by intravenous infusion only. Each vial contains 500 mg of mycophenolate mofetil equivalent to 542 mg of mycophenolate mofetil hydrochloride. The inactive ingredients are polysorbate 80, 25 mg, and citric acid, 5 mg. Sodium hydroxide or hydrochloric acid may have been used in the manufacture of CELLCEPT Intravenous to adjust the pH. Reconstitution and dilution with 5% Dextrose Injection USP yields a slightly yellow solution of MMF, 6 mg/mL [see Dosage and Administration (2.6)].

12 CLINICAL PHARMACOLOGY

12.1 Mechanism of Action

Mycophenolate mofetil (MMF) is absorbed following oral administration and hydrolyzed to mycophenolic acid (MPA), the active metabolite. MPA is a selective uncompetitive inhibitor of the two isoforms (type I and type II) of inosine monophosphate dehydrogenase (IMPDH) leading to inhibition of the de novo pathway of guanosine nucleotide synthesis and blocks DNA synthesis. The mechanism of action of MPA is multifaceted and includes effects on cellular checkpoints responsible for metabolic programming of lymphocytes. MPA shifts transcriptional activities in lymphocytes from a proliferative state to catabolic processes. In vitro studies suggest that MPA modulates transcriptional activities in human CD4^+ T-lymphocytes by suppressing the Akt/mTOR and STAT5 pathways that are relevant to metabolism and survival, leading to an anergic state of T-cells whereby the cells become less responsive to antigenic stimulation. Additionally, MPA enhanced the expression of negative co-stimulators such as CD70, PD-1, CTLA-4, and transcription factor FoxP3 as well as decreased the expression of positive co-stimulators CD27 and CD28.

MPA decreases proliferative responses of T- and B-lymphocytes to both mitogenic and allo-antigenic stimulation, antibody responses, as well as the production of cytokines from lymphocytes and monocytes such as GM-CSF, IFN-ɣ, IL-17, and TNF-α. Additionally, MPA prevents the glycosylation of lymphocyte and monocyte glycoproteins that are involved in intercellular adhesion to endothelial cells and may inhibit recruitment of leukocytes into sites of inflammation and graft rejection.

Overall, the effect of MPA is cytostatic and reversible.

12.2 Pharmacodynamics

There is a lack of information regarding the pharmacodynamic effects of MMF.

12.3 Pharmacokinetics

Absorption

Following oral and intravenous administration, MMF undergoes complete conversion to MPA, the active metabolite. In 12 healthy volunteers, the mean absolute bioavailability of oral MMF relative to intravenous MMF was 94%. Two 500 mg CELLCEPT tablets have been shown to be bioequivalent to four 250 mg CELLCEPT capsules. Five mL of the 200 mg/mL constituted CELLCEPT oral suspension have been shown to be bioequivalent to four 250 mg capsules.

The mean (±SD) pharmacokinetic parameters estimates for MPA following the administration of MMF given as single doses to healthy volunteers, and multiple doses to kidney, heart, and liver transplant patients, are shown in Table 10. The area under the plasma-concentration time curve (AUC) for MPA appears to increase in a dose-proportional fashion in kidney transplant patients receiving multiple oral doses of MMF up to a daily dose of 3 g (1.5g twice daily) (see Table 10).

Table 10 Pharmacokinetic Parameters for MPA [mean (±SD)] Following Administration of MMF to Healthy Volunteers (Single Dose), and Kidney, Heart, and Liver Transplant Patients (Multiple Doses)
Healthy Volunteers | Dose/Route | Tmax (h) | Cmax (mcg/mL) | Total AUC (mcg∙h/mL)
Single dose | 1 g/oral | 0.80 (±0.36) (n=129) | 24.5 (±9.5) (n=129) | 63.9 (±16.2) (n=117)
Kidney Transplant Patients (twice daily dosing) Time After Transplantation | Dose/Route | Tmax (h) | Cmax (mcg/mL) | Interdosing Interval AUC(0-12h) (mcg∙h/mL)
5 days | 1 g/iv | 1.58 (±0.46) (n=31) | 12.0 (±3.82) (n=31) | 40.8 (±11.4) (n=31)
6 days | 1 g/oral | 1.33 (±1.05) (n=31) | 10.7 (±4.83) (n=31) | 32.9 (±15.0) (n=31)
Early (Less than 40 days) | 1 g/oral | 1.31 (±0.76) (n=25) | 8.16 (±4.50) (n=25) | 27.3 (±10.9) (n=25)
Early (Less than 40 days) | 1.5 g/oral | 1.21 (±0.81) (n=27) | 13.5 (±8.18) (n=27) | 38.4 (±15.4) (n=27)
Late (Greater than 3 months) | 1.5 g/oral | 0.90 (±0.24) (n=23) | 24.1 (±12.1) (n=23) | 65.3 (±35.4) (n=23)
Heart transplant Patients (twice daily dosing) Time After Transplantation | Dose/Route | Tmax (h) | Cmax (mcg/mL) | Interdosing Interval AUC(0-12h) (mcg∙h/mL)
Early (Day before discharge) | 1.5 g/oral | 1.8 (±1.3) (n=11) | 11.5 (±6.8) (n=11) | 43.3 (±20.8) (n=9)
Late (Greater than 6 months) | 1.5 g/oral | 1.1 (±0.7) (n=52) | 20.0 (±9.4) (n=52) | 54.1 [AUC(0-12h) values quoted are extrapolated from data from samples collected over 4 hours.] (±20.4) (n=49)
Liver transplant Patients (twice daily dosing) Time After Transplantation | Dose/Route | Tmax (h) | Cmax (mcg/mL) | Interdosing Interval AUC(0-12h) (mcg∙h/mL)
4 to 9 days | 1 g/iv | 1.50 (±0.517) (n=22) | 17.0 (±12.7) (n=22) | 34.0 (±17.4) (n=22)
Early (5 to 8 days) | 1.5 g/oral | 1.15 (±0.432) (n=20) | 13.1 (±6.76) (n=20) | 29.2 (±11.9) (n=20)
Late (Greater than 6 months) | 1.5 g/oral | 1.54 (±0.51) (n=6) | 19.3 (±11.7) (n=6) | 49.3 (±14.8) (n=6)

In the early post-transplant period (less than 40 days post-transplant), kidney, heart, and liver transplant patients had mean MPA AUCs approximately 20% to 41% lower and mean Cmax approximately 32% to 44% lower compared to the late transplant period (i.e., 3 to 6 months post-transplant) (non-stationarity in MPA pharmacokinetics).

Mean MPA AUC values following administration of 1 g twice daily intravenous CELLCEPT over 2 hours to kidney transplant patients for 5 days were about 24% higher than those observed after oral administration of a similar dose in the immediate post-transplant phase.

In liver transplant patients, administration of 1 g twice daily intravenous CELLCEPT followed by 1.5 g twice daily oral CELLCEPT resulted in mean MPA AUC estimates similar to those found in kidney transplant patients administered 1 g CELLCEPT twice daily.

Effect of Food

Food (27 g fat, 650 calories) had no effect on the extent of absorption (MPA AUC) of MMF when administered at doses of 1.5 g twice daily to kidney transplant patients. However, MPA Cmax was decreased by 40% in the presence of food [see Dosage and Administration (2.1)].

Distribution

The mean (±SD) apparent volume of distribution of MPA in 12 healthy volunteers was approximately 3.6 (±1.5) L/kg. At clinically relevant concentrations, MPA is 97% bound to plasma albumin. The phenolic glucuronide metabolite of MPA (MPAG) is 82% bound to plasma albumin at MPAG concentration ranges that are normally seen in stable kidney transplant patients; however, at higher MPAG concentrations (observed in patients with kidney impairment or delayed kidney graft function), the binding of MPA may be reduced as a result of competition between MPAG and MPA for protein binding. Mean blood to plasma ratio of radioactivity concentrations was approximately 0.6 indicating that MPA and MPAG do not extensively distribute into the cellular fractions of blood.

In vitro studies to evaluate the effect of other agents on the binding of MPA to human serum albumin (HSA) or plasma proteins showed that salicylate (at 25 mg/dL with human serum albumin) and MPAG (at ≥ 460 mcg/mL with plasma proteins) increased the free fraction of MPA. MPA at concentrations as high as 100 mcg/mL had little effect on the binding of warfarin, digoxin or propranolol, but decreased the binding of theophylline from 53% to 45% and phenytoin from 90% to 87%.

Elimination

Mean (±SD) apparent half-life and plasma clearance of MPA are 17.9 (±6.5) hours and 193 (±48) mL/min following oral administration and 16.6 (±5.8) hours and 177 (±31) mL/min following intravenous administration, respectively.

Metabolism

The parent drug, MMF, can be measured systemically during the intravenous infusion; however, approximately 5 minutes after the infusion is stopped or after oral administration, MMF concentrations are below the limit of quantitation (0.4 mcg/mL).

Metabolism to MPA occurs pre-systemically after oral dosing. MPA is metabolized principally by glucuronyl transferase to form MPAG, which is not pharmacologically active. In vivo, MPAG is converted to MPA during enterohepatic recirculation. The following metabolites of the 2-hydroxyethyl-morpholino moiety are also recovered in the urine following oral administration of MMF to healthy subjects: N-(2-carboxymethyl)-morpholine, N-(2-hydroxyethyl)-morpholine, and the N-oxide of N-(2-hydroxyethyl)-morpholine.

Due to the enterohepatic recirculation of MPAG/MPA, secondary peaks in the plasma MPA concentration-time profile are usually observed 6 to 12 hours post-dose. Bile sequestrants, such as cholestyramine, reduce MPA AUC by interfering with this enterohepatic recirculation of the drug [see Overdosage (10) and Drug Interaction Studies below].

Excretion

Negligible amount of drug is excreted as MPA (less than 1% of dose) in the urine. Orally administered radiolabeled MMF resulted in complete recovery of the administered dose, with 93% of the administered dose recovered in the urine and 6% recovered in feces. Most (about 87%) of the administered dose is excreted in the urine as MPAG. At clinically encountered concentrations, MPA and MPAG are usually not removed by hemodialysis. However, at high MPAG plasma concentrations (> 100 mcg/mL), small amounts of MPAG are removed.

Increased plasma concentrations of MMF metabolites (MPA 50% increase and MPAG about a 3-fold to 6-fold increase) are observed in patients with renal insufficiency [see Specific Populations].

Specific Populations

Patients with Renal Impairment

The mean (±SD) pharmacokinetic parameters for MPA following the administration of oral MMF given as single doses to non-transplant subjects with renal impairment are presented in Table 11.

In a single-dose study, MMF was administered as a capsule or as an intravenous infusion over 40 minutes. Plasma MPA AUC observed after oral dosing to volunteers with severe chronic renal impairment (GFR < 25 mL/min/1.73 m^2) was about 75% higher relative to that observed in healthy volunteers (GFR > 80 mL/min/1.73 m^2). In addition, the single-dose plasma MPAG AUC was 3-fold to 6-fold higher in volunteers with severe renal impairment than in volunteers with mild renal impairment or healthy volunteers, consistent with the known renal elimination of MPAG. No data are available on the safety of long-term exposure to this level of MPAG.

Plasma MPA AUC observed after single-dose (1 g) intravenous dosing to volunteers (n=4) with severe chronic renal impairment (GFR < 25 mL/min/1.73 m^2) was 62.4 mcg∙h/mL (±19.3). Multiple dosing of MMF in patients with severe chronic renal impairment has not been studied.

Patients with Delayed Graft Function or Nonfunction

In patients with delayed renal graft function post-transplant, mean MPA AUC(0-12h) was comparable to that seen in post-transplant patients without delayed renal graft function. There is a potential for a transient increase in the free fraction and concentration of plasma MPA in patients with delayed renal graft function. However, dose adjustment does not appear to be necessary in patients with delayed renal graft function. Mean plasma MPAG AUC(0-12h) was 2-fold to 3-fold higher than in post-transplant patients without delayed renal graft function [see Dosage and Administration (2.5)].

In eight patients with primary graft non-function following kidney transplantation, plasma concentrations of MPAG accumulated about 6-fold to 8-fold after multiple dosing for 28 days. Accumulation of MPA was about 1-fold to 2-fold.

The pharmacokinetics of MMF are not altered by hemodialysis. Hemodialysis usually does not remove MPA or MPAG. At high concentrations of MPAG (> 100 mcg/mL), hemodialysis removes only small amounts of MPAG.

Patients with Hepatic Impairment

The mean (± SD) pharmacokinetic parameters for MPA following the administration of oral MMF given as single doses to non-transplant subjects with hepatic impairment is presented in Table 11.

In a single-dose (1 g oral) study of 18 volunteers with alcoholic cirrhosis and 6 healthy volunteers, hepatic MPA glucuronidation processes appeared to be relatively unaffected by hepatic parenchymal disease when pharmacokinetic parameters of healthy volunteers and alcoholic cirrhosis patients within this study were compared. However, it should be noted that for unexplained reasons, the healthy volunteers in this study had about a 50% lower AUC as compared to healthy volunteers in other studies, thus making comparisons between volunteers with alcoholic cirrhosis and healthy volunteers difficult. In a single-dose (1 g intravenous) study of 6 volunteers with severe hepatic impairment (aminopyrine breath test less than 0.2% of dose) due to alcoholic cirrhosis, MMF was rapidly converted to MPA. MPA AUC was 44.1 mcg∙h/mL (±15.5).

Table 11 Pharmacokinetic Parameters for MPA [mean (±SD)] Following Single Doses of MMF Capsules in Chronic Renal and Hepatic Impairment
Pharmacokinetic Parameters for Renal Impairment
 | Dose | Tmax (h) | Cmax (mcg/mL) | AUC(0-96h) (mcg∙h/mL)
Healthy Volunteers GFR greater than 80 mL/min/1.73 m^2 (n=6) | 1 g | 0.75 (±0.27) | 25.3 (±7.99) | 45.0 (±22.6)
Mild Renal Impairment GFR 50 to 80 mL/min/1.73 m^2 (n=6) | 1 g | 0.75 (±0.27) | 26.0 (±3.82) | 59.9 (±12.9)
Moderate Renal Impairment GFR 25 to 49 mL/min/1.73 m^2 (n=6) | 1 g | 0.75 (±0.27) | 19.0 (±13.2) | 52.9 (±25.5)
Severe Renal Impairment GFR less than 25 mL/min/1.73 m^2 (n=7) | 1 g | 1.00 (±0.41) | 16.3 (±10.8) | 78.6 (±46.4)
Pharmacokinetic Parameters for Hepatic Impairment
 | Dose | Tmax (h) | Cmax (mcg/mL) | AUC(0-48h) (mcg∙h/mL)
Healthy Volunteers (n=6) | 1 g | 0.63 (±0.14) | 24.3 (±5.73) | 29.0 (±5.78)
Alcoholic Cirrhosis (n=18) | 1 g | 0.85 (±0.58) | 22.4 (±10.1) | 29.8 (±10.7)

Pediatric Patients

The pharmacokinetic parameters of MPA and MPAG have been evaluated in 55 pediatric patients (ranging from 1 year to 18 years of age) receiving CELLCEPT oral suspension at a dose of 600 mg/m^2 twice daily (up to a maximum of 1 g twice daily) after allogeneic kidney transplantation. The pharmacokinetic data for MPA is provided in Table 12.

Table 12 Mean (±SD) Computed Pharmacokinetic Parameters for MPA by Age and Time after Allogeneic Kidney Transplantation
Age Group | (n) | Time | Tmax (h) |  | Dose Adjusted [adjusted to a dose of 600 mg/m^2] Cmax (mcg/mL) |  | Dose Adjusted AUC0-12 (mcg∙h/mL)
 |  | Early (Day 7)
1 to less than 2 yr | (6) [a subset of 1 to <6 yr] |  | 3.03 | (4.70) | 10.3 | (5.80) | 22.5 | (6.66)
1 to less than 6 yr | (17) |  | 1.63 | (2.85) | 13.2 | (7.16) | 27.4 | (9.54)
6 to less than 12 yr | (16) |  | 0.940 | (0.546) | 13.1 | (6.30) | 33.2 | (12.1)
12 to 18 yr | (21) |  | 1.16 | (0.830) | 11.7 | (10.7) | 26.3 | (9.14) [n=20]
 |  | Late (Month 3)
1 to less than 2 yr | (4) |  | 0.725 | (0.276) | 23.8 | (13.4) | 47.4 | (14.7)
1 to less than 6 yr | (15) |  | 0.989 | (0.511) | 22.7 | (10.1) | 49.7 | (18.2)
6 to less than 12 yr | (14) |  | 1.21 | (0.532) | 27.8 | (14.3) | 61.9 | (19.6)
12 to 18 yr | (17) |  | 0.978 | (0.484) | 17.9 | (9.57) | 53.6 | (20.3) [n=16]
 |  | Late (Month 9)
1 to less than 2 yr | (4) |  | 0.604 | (0.208) | 25.6 | (4.25) | 55.8 | (11.6)
1 to less than 6 yr | (12) |  | 0.869 | (0.479) | 30.4 | (9.16) | 61.0 | (10.7)
6 to less than 12 yr | (11) |  | 1.12 | (0.462) | 29.2 | (12.6) | 66.8 | (21.2)
12 to 18 yr | (14) |  | 1.09 | (0.518) | 18.1 | (7.29) | 56.7 | (14.0)

The CELLCEPT oral suspension dose of 600 mg/m^2 twice daily (up to a maximum of 1 g twice daily) achieved mean MPA AUC values in pediatric patients similar to those seen in adult kidney transplant patients receiving CELLCEPT capsules at a dose of 1 g twice daily in the early post-transplant period. There was wide variability in the data. As observed in adults, early post-transplant MPA AUC values were approximately 45% to 53% lower than those observed in the later post-transplant period (>3 months). MPA AUC values were similar in the early and late post-transplant period across the 1 to 18-year age range.

A comparison of dose-normalized (to 600 mg/m^2) MPA AUC values in 12 pediatric kidney transplant patients less than 6 years of age at 9 months post-transplant with those values in 7 pediatric liver transplant patients [median age 17 months (range: 10 – 60 months)] and at 6 months and beyond post-transplant revealed that, at the same dose, there were on average 23% lower AUC values in the pediatric liver compared to pediatric kidney patients. This is consistent with the need for higher dosing in adult liver transplant patients compared to kidney transplant patients to achieve the same exposure.

In adult transplant patients administered the same dosage of CELLCEPT, there is similar MPA exposure among kidney transplant and heart transplant patients. Based on the established similarity in MPA exposure between pediatric kidney transplant and adult kidney transplant patients at their respective approved doses, it is expected that MPA exposure at the recommended dosage will be similar in pediatric heart transplant and adult heart transplant patients.

Male and Female Patients

Data obtained from several studies were pooled to look at any gender-related differences in the pharmacokinetics of MPA (data were adjusted to 1 g oral dose). Mean (±SD) MPA AUC (0-12h) for males (n=79) was 32.0 (±14.5) and for females (n=41) was 36.5 (±18.8) mcg∙h/mL while mean (±SD) MPA Cmax was 9.96 (±6.19) in the males and 10.6 (±5.64) mcg/mL in the females. These differences are not of clinical significance.

Geriatric Patients

The pharmacokinetics of mycophenolate mofetil and its metabolites have not been found to be altered in geriatric transplant patients when compared to younger transplant patients.

Drug Interaction Studies

Acyclovir

Coadministration of MMF (1 g) and acyclovir (800 mg) to 12 healthy volunteers resulted in no significant change in MPA AUC and Cmax. However, MPAG and acyclovir plasma AUCs were increased 10.6% and 21.9%, respectively.

Antacids with Magnesium and Aluminum Hydroxides

Absorption of a single dose of MMF (2 g) was decreased when administered to 10 rheumatoid arthritis patients also taking Maalox® TC (10 mL qid). The Cmax and AUC(0-24h) for MPA were 33% and 17% lower, respectively, than when MMF was administered alone under fasting conditions.

Proton Pump Inhibitors (PPIs)

Coadministration of PPIs (e.g., lansoprazole, pantoprazole) in single doses to healthy volunteers and multiple doses to transplant patients receiving CELLCEPT has been reported to reduce the exposure to MPA. An approximate reduction of 30 to 70% in the Cmax and 25% to 35% in the AUC of MPA has been observed, possibly due to a decrease in MPA solubility at an increased gastric pH.

Cholestyramine

Following single-dose administration of 1.5 g MMF to 12 healthy volunteers pretreated with 4 g three times a day of cholestyramine for 4 days, MPA AUC decreased approximately 40%. This decrease is consistent with interruption of enterohepatic recirculation which may be due to binding of recirculating MPAG with cholestyramine in the intestine.

Cyclosporine

Cyclosporine (Sandimmune®) pharmacokinetics (at doses of 275 to 415 mg/day) were unaffected by single and multiple doses of 1.5 g twice daily of MMF in 10 stable kidney transplant patients. The mean (±SD) AUC(0-12h) and Cmax of cyclosporine after 14 days of multiple doses of MMF were 3290 (±822) ng∙h/mL and 753 (±161) ng/mL, respectively, compared to 3245 (±1088) ng∙h/mL and 700 (±246) ng/mL, respectively, 1 week before administration of MMF.

Cyclosporine A interferes with MPA enterohepatic recirculation. In kidney transplant patients, mean MPA exposure (AUC(0-12h)) was approximately 30-50% greater when MMF was administered without cyclosporine compared with when MMF was coadministered with cyclosporine. This interaction is due to cyclosporine inhibition of multidrug-resistance-associated protein 2 (MRP-2) transporter in the biliary tract, thereby preventing the excretion of MPAG into the bile that would lead to enterohepatic recirculation of MPA. This information should be taken into consideration when MMF is used without cyclosporine.

Drugs Affecting Glucuronidation

Concomitant administration of drugs inhibiting glucuronidation of MPA may increase MPA exposure (e.g., increase of MPA AUC (0-∞) by 35% was observed with concomitant administration of isavuconazole).

Concomitant administration of telmisartan and CELLCEPT resulted in an approximately 30% decrease in MPA concentrations. Telmisartan changes MPA's elimination by enhancing PPAR gamma (peroxisome proliferator-activated receptor gamma) expression, which in turn results in an enhanced UGT1A9 expression and glucuronidation activity.

Ganciclovir

Following single-dose administration to 12 stable kidney transplant patients, no pharmacokinetic interaction was observed between MMF (1.5 g) and intravenous ganciclovir (5 mg/kg). Mean (±SD) ganciclovir AUC and Cmax (n=10) were 54.3 (±19.0) mcg∙h/mL and 11.5 (±1.8) mcg/mL, respectively, after coadministration of the two drugs, compared to 51.0 (±17.0) mcg∙h/mL and 10.6 (±2.0) mcg/mL, respectively, after administration of intravenous ganciclovir alone. The mean (±SD) AUC and Cmax of MPA (n=12) after coadministration were 80.9 (±21.6) mcg∙h/mL and 27.8 (±13.9) mcg/mL, respectively, compared to values of 80.3 (±16.4) µg∙h/mL and 30.9 (±11.2) mcg/mL, respectively, after administration of MMF alone.

Oral Contraceptives

A study of coadministration of CELLCEPT (1 g twice daily) and combined oral contraceptives containing ethinylestradiol (0.02 mg to 0.04 mg) and levonorgestrel (0.05 mg to 0.20 mg), desogestrel (0.15 mg) or gestodene (0.05 mg to 0.10 mg) was conducted in 18 women with psoriasis over 3 consecutive menstrual cycles. Mean serum levels of LH, FSH and progesterone were not significantly affected. Mean AUC(0-24h) was similar for ethinylestradiol and 3-keto desogestrel; however, mean levonorgestrel AUC(0-24h) significantly decreased by about 15%. There was large inter-patient variability (%CV in the range of 60% to 70%) in the data, especially for ethinylestradiol.

Sevelamer

Concomitant administration of sevelamer and MMF in adult and pediatric patients decreased the mean MPA Cmax and AUC (0-12h) by 36% and 26% respectively.

Antimicrobials

Antimicrobials eliminating beta-glucuronidase-producing bacteria in the intestine (e.g. aminoglycoside, cephalosporin, fluoroquinolone, and penicillin classes of antimicrobials) may interfere with the MPAG/MPA enterohepatic recirculation thus leading to reduced systemic MPA exposure. Information concerning antibiotics is as follows:

- Trimethoprim/Sulfamethoxazole: Following single-dose administration of MMF (1.5 g) to 12 healthy male volunteers on day 8 of a 10-day course of trimethoprim 160 mg/sulfamethoxazole 800 mg administered twice daily, no effect on the bioavailability of MPA was observed. The mean (±SD) AUC and Cmax of MPA after concomitant administration were 75.2 (±19.8) mcg∙h/mL and 34.0 (±6.6) µg/mL, respectively, compared to 79.2 (±27.9) mcg∙h/mL and 34.2 (±10.7) mcg/mL, respectively, after administration of MMF alone.
- Norfloxacin and Metronidazole: Following single-dose administration of MMF (1 g) to 11 healthy volunteers on day 4 of a 5-day course of a combination of norfloxacin and metronidazole, the mean MPA AUC(0-48h) was significantly reduced by 33% compared to the administration of MMF alone (p<0.05). The mean (±SD) MPA AUC(0-48h) after coadministration of MMF with norfloxacin or metronidazole separately was 48.3 (±24) mcg∙h/mL and 42.7 (±23) mcg∙h/mL, respectively, compared with 56.2 (±24) mcg∙h/mL after administration of MMF alone.
- Ciprofloxacin and Amoxicillin Plus Clavulanic Acid: A total of 64 CELLCEPT-treated kidney transplant recipients received either oral ciprofloxacin 500 mg twice daily or amoxicillin plus clavulanic acid 375 mg three times daily for 7 or at least 14 days, respectively. Approximately 50% reductions in median trough MPA concentrations (pre-dose) from baseline (CELLCEPT alone) were observed in 3 days following commencement of oral ciprofloxacin or amoxicillin plus clavulanic acid. These reductions in trough MPA concentrations tended to diminish within 14 days of antimicrobial therapy and ceased within 3 days of discontinuation of antibiotics.
- Rifampin: In a single heart-lung transplant patient, after correction for dose, a 67% decrease in MPA exposure (AUC(0-12h)) has been observed with concomitant administration of MMF and rifampin.

13 NONCLINICAL TOXICOLOGY

13.1 Carcinogenesis, Mutagenesis, Impairment of Fertility

In a 104-week oral carcinogenicity study in mice, MMF in daily doses up to 180 mg/kg was not tumorigenic. The highest dose tested was 0.2 times the recommended clinical dose (2 g/day) in renal transplant patients and 0.15 times the recommended clinical dose (3 g/day) in cardiac transplant patients when corrected for differences in body surface area (BSA). In a 104-week oral carcinogenicity study in rats, MMF in daily doses up to 15 mg/kg was not tumorigenic. The highest dose was 0.035 times the recommended clinical dose in kidney transplant patients and 0.025 times the recommended clinical dose in heart transplant patients when corrected for BSA. While these animal doses were lower than those given to patients, they were maximal in those species and were considered adequate to evaluate the potential for human risk [see Warnings and Precautions (5.2)].

The genotoxic potential of MMF was determined in five assays. MMF was genotoxic in the mouse lymphoma/thymidine kinase assay and the in vivo mouse micronucleus assay. MMF was not genotoxic in the bacterial mutation assay, the yeast mitotic gene conversion assay or the Chinese hamster ovary cell chromosomal aberration assay.

MMF had no effect on fertility of male rats at oral doses up to 20 mg/kg/day. This dose represents 0.05 times the recommended clinical dose in renal transplant patients and 0.03 times the recommended clinical dose in cardiac transplant patients when corrected for BSA. In a female fertility and reproduction study conducted in rats, oral doses of 4.5 mg/kg/day caused malformations (principally of the head and eyes) in the first generation offspring in the absence of maternal toxicity. This dose was 0.01 times the recommended clinical dose in renal transplant patients and 0.005 times the recommended clinical dose in cardiac transplant patients when corrected for BSA. No effects on fertility or reproductive parameters were evident in the dams or in the subsequent generation.

14 CLINICAL STUDIES

14.1 Kidney Transplantation

Adults

The three de novo kidney transplantation studies compared two dose levels of oral CELLCEPT (1 g twice daily and 1.5 g twice daily) with azathioprine (2 studies) or placebo (1 study) to prevent acute rejection episodes. One of the two studies with azathioprine (AZA) control arm also included anti-thymocyte globulin (ATGAM®) induction therapy. The geographic location of the investigational sites of these studies are included in Table 13.

In all three de novo kidney transplantation studies, the primary efficacy endpoint was the proportion of patients in each treatment group who experienced treatment failure within the first 6 months after transplantation. Treatment failure was defined as biopsy-proven acute rejection on treatment or the occurrence of death, graft loss or early termination from the study for any reason without prior biopsy-proven rejection.

CELLCEPT, in combination with corticosteroids and cyclosporine, reduced (statistically significant at 0.05 level) the incidence of treatment failure within the first 6 months following transplantation (Table 13). Patients who prematurely discontinued treatment were followed for the occurrence of death or graft loss, and the cumulative incidence of graft loss and patient death combined are summarized in Table 14. Patients who prematurely discontinued treatment were not followed for the occurrence of acute rejection after termination.

Table 13 Treatment Failure in De Novo Kidney Transplantation Studies
USA Study | CELLCEPT 2 g/day | CELLCEPT 3 g/day | AZA 1 to 2 mg/kg/day
(N=499 patients) | (n=167 patients) | (n=166 patients) | (n=166 patients)
 | All 3 groups received anti-thymocyte globulin induction, cyclosporine and corticosteroids
All treatment failures | 31.1% | 31.3% | 47.6%
Early termination without prior acute rejection | 9.6% | 12.7% | 6.0%
Biopsy-proven rejection episode on treatment | 19.8% | 17.5% | 38.0%
Europe/Canada/Australia Study (N=503 patients) | CELLCEPT 2 g/day (n=173 patients) | CELLCEPT 3 g/day (n=164 patients) | AZA 100 to 150 mg/day (n=166 patients)
Europe/Canada/Australia Study (N=503 patients) | No induction treatment administered; all 3 groups received cyclosporine and corticosteroids.
All treatment failures | 38.2% | 34.8% | 50.0%
Early termination without prior acute rejection | 13.9% | 15.2% | 10.2%
Biopsy-proven rejection episode on treatment | 19.7% | 15.9% | 35.5%
Europe Study | CELLCEPT 2 g/day | CELLCEPT 3 g/day | Placebo
(N=491 patients) | (n=165 patients) | (n=160 patients) | (n=166 patients)
 | No induction treatment administered; all 3 groups received cyclosporine and corticosteroids.
All treatment failures | 30.3% | 38.8% | 56.0%
Early termination without prior acute rejection | 11.5% | 22.5% | 7.2%
Biopsy-proven rejection episode on treatment | 17.0% | 13.8% | 46.4%
*Does not include death and graft loss as reason for early termination.

No advantage of CELLCEPT at 12 months with respect to graft loss or patient death (combined) was established (Table 14). Numerically, patients receiving CELLCEPT 2 g/day and 3 g/day experienced a better outcome than controls in all three studies; patients receiving CELLCEPT 2 g/day experienced a better outcome than CELLCEPT 3 g/day in two of the three studies. Patients in all treatment groups who terminated treatment early were found to have a poor outcome with respect to graft loss or patient death at 1 year.

Table 14 De Novo Kidney Transplantation Studies Cumulative Incidence of Combined Graft Loss or Patient Death at 12 Months
Study | CELLCEPT 2 g/day | CELLCEPT 3 g/day | Control (AZA or Placebo)
USA | 8.5% | 11.5% | 12.2%
Europe/Canada/Australia | 11.7% | 11.0% | 13.6%
Europe | 8.5% | 10.0% | 11.5%

Pediatrics- De Novo Kidney transplantation PK Study with Long Term Follow-Up

One open-label, safety and pharmacokinetic study of CELLCEPT oral suspension 600 mg/m^2 twice daily (up to 1 g twice daily) in combination with cyclosporine and corticosteroids was performed at centers in the United States (9), Europe (5) and Australia (1) in 100 pediatric patients (3 months to 18 years of age) for the prevention of renal allograft rejection. CELLCEPT was well tolerated in pediatric patients [see Adverse Reactions (6.1)], and the pharmacokinetics profile was similar to that seen in adult patients dosed with 1 g twice daily CELLCEPT capsules [see Clinical Pharmacology (12.3)]. The rate of biopsy-proven rejection was similar across the age groups (3 months to <6 years, 6 years to <12 years, 12 years to 18 years). The overall biopsy-proven rejection rate at 6 months was comparable to adults. The combined incidence of graft loss (5%) and patient death (2%) at 12 months post-transplant was similar to that observed in adult kidney transplant patients.

14.2 Heart Transplantation

A double-blind, randomized, comparative, parallel-group, multicenter study in primary de novo heart transplant recipients was performed at centers in the United States (20), in Canada (1), in Europe (5) and in Australia (2). The total number of patients enrolled (ITT population) was 650; 72 never received study drug and 578 received study drug (Safety Population). Patients received CELLCEPT 1.5 g twice daily (n=289) or AZA 1.5 to 3 mg/kg/day (n=289), in combination with cyclosporine (Sandimmune® or Neoral®) and corticosteroids as maintenance immunosuppressive therapy. The two primary efficacy endpoints were: (1) the proportion of patients who, after transplantation, had at least one endomyocardial biopsy-proven rejection with hemodynamic compromise, or were re-transplanted or died, within the first 6 months, and (2) the proportion of patients who died or were re-transplanted during the first 12 months following transplantation. Patients who prematurely discontinued treatment were followed for the occurrence of allograft rejection for up to 6 months and for the occurrence of death for 1 year.

The analyses of the endpoints showed:

- Rejection: No difference was established between CELLCEPT and AZA with respect to biopsy-proven rejection with hemodynamic compromise.
- Survival: CELLCEPT was shown to be at least as effective as AZA in preventing death or re-transplantation at 1 year (see Table 15).

Table 15 De Novo Heart Transplantation Study Rejection at 6 Months/Death or Re-transplantation at 1 Year
 | All Patients (ITT) |  | Treated Patients
 | AZA N = 323 | CELLCEPT N = 327 | AZA N = 289 | CELLCEPT N = 289
Biopsy-proven rejection with hemodynamic compromise at 6 months [Hemodynamic compromise occurred if any of the following criteria were met: pulmonary capillary wedge pressure ≥20 mm or a 25% increase; cardiac index <2.0 L/min/m^2 or a 25% decrease; ejection fraction ≤30%; pulmonary artery oxygen saturation ≤60% or a 25% decrease; presence of new S3 gallop; fractional shortening was ≤20% or a 25% decrease; inotropic support required to manage the clinical condition.] | 121 (38%) | 120 (37%) | 100 (35%) | 92 (32%)
Death or re-transplantation at 1 year | 49 (15.2%) | 42 (12.8%) | 33 (11.4%) | 18 (6.2%)

14.3 Liver Transplantation

A double-blind, randomized, comparative, parallel-group, multicenter study in primary hepatic transplant recipients was performed at centers in the United States (16), in Canada (2), in Europe (4) and in Australia (1). The total number of patients enrolled was 565. Per protocol, patients received CELLCEPT 1 g twice daily intravenously for up to 14 days followed by CELLCEPT 1.5 g twice daily orally or AZA 1 to 2 mg/kg/day intravenously followed by AZA 1 to 2 mg/kg/day orally, in combination with cyclosporine (Neoral®) and corticosteroids as maintenance immunosuppressive therapy. The actual median oral dose of AZA on study was 1.5 mg/kg/day (range of 0.3 to 3.8 mg/kg/day) initially and 1.26 mg/kg/day (range of 0.3 to 3.8 mg/kg/day) at 12 months. The two primary endpoints were: (1) the proportion of patients who experienced, in the first 6 months post-transplantation, one or more episodes of biopsy-proven and treated rejection or death or re-transplantation, and (2) the proportion of patients who experienced graft loss (death or re-transplantation) during the first 12 months post-transplantation. Patients who prematurely discontinued treatment were followed for the occurrence of allograft rejection and for the occurrence of graft loss (death or re-transplantation) for 1 year.

In combination with corticosteroids and cyclosporine, CELLCEPT demonstrated a lower rate of acute rejection at 6 months and a similar rate of death or re-transplantation at 1 year compared to AZA (Table 16).

Table 16 De Novo Liver Transplantation Study Rejection at 6 Months/Death or Retransplantation at 1 Year
 | AZA N = 287 | CELLCEPT N = 278
Biopsy-proven, treated rejection at 6 months (includes death or re-transplantation) | 137 (47.7%) | 107 (38.5%)
Death or re-transplantation at 1 year | 42 (14.6%) | 41 (14.7%)

15 REFERENCES

1. "OSHA Hazardous Drugs." OSHA. http://www.osha.gov/SLTC/hazardousdrugs/index.html

16 HOW SUPPLIED/STORAGE AND HANDLING

16.1 Handling and Disposal

Mycophenolate mofetil (MMF) has demonstrated teratogenic effects in humans [see Warnings and Precautions (5.1) and Use in Specific Populations (8.1)]. CELLCEPT tablets should not be crushed and CELLCEPT capsules should not be opened or crushed. Wearing disposable gloves is recommended during reconstitution and when wiping the outer surface of the bottle/cap and the table after reconstitution. Avoid inhalation or direct contact with skin or mucous membranes of the powder contained in CELLCEPT capsules, CELLCEPT Oral Suspension (before or after constitution), or CELLCEPT Intravenous (during or after preparation) [see Dosage and Administration (2.6)]. Follow applicable special handling and disposal procedures^1.

16.2 CELLCEPT (mycophenolate mofetil capsules) 250 mg

Capsules
Blue-brown, two-piece hard gelatin capsules, printed in black with "CELLCEPT 250" on the blue cap and "Roche" on the brown body.

Sizes

Bottle of 100

NDC 0004-0259-01

Bottle of 500

NDC 0004-0259-43

Storage
Store at 25°C (77°F); excursions permitted to 15°C to 30°C (59°F to 86°F)

16.3 CELLCEPT (mycophenolate mofetil tablets) 500 mg

Tablets
Lavender-colored, caplet-shaped, film-coated tablets engraved with "CELLCEPT 500" on one side and "Roche" on the other

Sizes

Bottle of 100

NDC 0004-0260-01

Bottle of 500

NDC 0004-0260-43

Storage and Dispensing Information:

- Store at 25°C (77°F); excursions permitted to 15°C to 30°C (59°F to 86°F).
- Dispense in light-resistant containers, such as the manufacturer's original containers.

16.4 CELLCEPT Oral Suspension (mycophenolate mofetil), for oral suspension

For oral suspension: 35 g mycophenolate mofetil, white to off-white powder blend for constitution to a white to off-white mixed-fruit flavor suspension

225 mL bottle with bottle adapter and 2 oral dispensers

NDC 0004-0261-29

Storage

- Store dry powder at 25°C (77°F); excursions permitted to 15°C to 30°C (59°F to 86°F).
- Store constituted suspension at 25°C (77°F); excursions permitted to 15°C to 30°C (59°F to 86°F) for up to 60 days. Storage in a refrigerator at 2°C to 8°C (36°F to 46°F) is acceptable. Do not freeze.

16.5 CELLCEPT Intravenous (mycophenolate mofetil for injection)

For injection: 500 mg mycophenolate mofetil in a 20 mL sterile single-dose vial cartons of 4 vials

Cartons of 4 single-dose vials

NDC 0004-0298-09

Storage

- Store powder and reconstituted infusion solution at 25°C (77°F); excursions permitted to 15°C to 30°C (59°F to 86°F).

17 PATIENT COUNSELING INFORMATION

Advise the patient to read the FDA-approved patient labeling (Medication Guide and Instructions for Use).

17.1 Embryofetal Toxicity

Pregnancy loss and malformations

- Inform females of reproductive potential and pregnant women that use of CELLCEPT during pregnancy is associated with an increased risk of first trimester pregnancy loss and an increased risk of congenital malformations. Advise that they must use an acceptable form of contraception [see Warnings and Precautions (5.1), Use in Specific Populations (8.1, 8.3)].
- Encourage pregnant women to enroll in the Pregnancy Exposure Registry. This registry monitors pregnancy outcomes in women exposed to mycophenolate [see Use in Specific Populations (8.1)].

Contraception

- Discuss pregnancy testing, pregnancy prevention and planning with females of reproductive potential [see Use in Specific Populations (8.3)].
- Females of reproductive potential must use an acceptable form of birth control during the entire CELLCEPT therapy and for 6 weeks after stopping CELLCEPT, unless the patient chooses abstinence. CELLCEPT may reduce effectiveness of oral contraceptives. Use of additional barrier contraceptive methods is recommended [see Use in Specific Populations (8.3)].
- For patients who are considering pregnancy, discuss appropriate alternative immunosuppressants with less potential for embryofetal toxicity. Risks and benefits of CELLCEPT should be discussed with the patient.
- Advise sexually active male patients and/or their partners to use effective contraception during the treatment of the male patient and for at least 90 days after cessation of treatment. This recommendation is based on findings of animal studies [see Use in Specific Populations (8.3), Nonclinical Toxicology (13.1)].

17.2 Development of Lymphoma and Other Malignancies

- Inform patients that they are at increased risk of developing lymphomas and other malignancies, particularly of the skin, due to immunosuppression [see Warnings and Precautions (5.2)].
- Advise patients to limit exposure to sunlight and ultraviolet (UV) light by wearing protective clothing and use of broad-spectrum sunscreen with high protection factor.

17.3 Increased Risk of Serious Infections

Inform patients that they are at increased risk of developing a variety of infections due to immunosuppression. Instruct them to contact their physician if they develop any of the signs and symptoms of infection explained in the Medication Guide [see Warnings and Precautions (5.3)].

17.4 Blood Dyscrasias

Inform patients that they are at increased risk for developing blood adverse effects such as anemia or low white blood cells. Advise patients to immediately contact their healthcare provider if they experience any evidence of infection, unexpected bruising, or bleeding, or any other manifestation of bone marrow suppression [see Warnings and Precautions (5.4)].

17.5 Gastrointestinal Tract Complications

Inform patients that CELLCEPT can cause gastrointestinal tract complications including bleeding, intestinal perforations, and gastric or duodenal ulcers. Advise the patient to contact their healthcare provider if they have symptoms of gastrointestinal bleeding, or sudden onset or persistent abdominal pain [see Warnings and Precautions (5.5)].

17.6 Acute Inflammatory Syndrome

Inform patients that acute inflammatory reactions have been reported in some patients who received CELLCEPT. Some reactions were severe, requiring hospitalization. Advise patients to contact their physician if they develop fever, joint stiffness, joint pain or muscle pains [see Warnings and Precautions (5.7)].

17.7 Hypersensitivity Reactions

Inform patients of the potential risk of hypersensitivity reactions. Advise patients to stop taking CELLCEPT and seek immediate medical attention if signs or symptoms of hypersensitivity reaction occur (such as swelling of face, lips, tongue, or throat; difficulty breathing or swallowing) [see Warnings and Precautions (5.8)].

17.8 Immunizations

Inform patients that CELLCEPT can interfere with the usual response to immunizations. Before seeking vaccines on their own, advise patients to discuss first with their physician [see Warnings and Precautions (5.9)].

17.9 Administration Instructions

- Advise patients not to crush CELLCEPT tablets and not to open CELLCEPT capsules.
- Advise patients to avoid inhalation or contact of the skin or mucous membranes with the powder contained in CELLCEPT capsules and with the oral suspension. If such contact occurs, they must wash the area of contact thoroughly with soap and water. In case of ocular contact, rinse eyes with plain water.
- Advise patients to take a missed dose as soon as they remember, except if it is closer than 2 hours to the next scheduled dose; in this case they should continue to take CELLCEPT at the usual times.

17.10 Blood Donation

Advise patients not to donate blood during therapy and for at least 6 weeks following discontinuation of CELLCEPT [see Warnings and Precautions (5.12)].

17.11Semen Donation

Advise males of childbearing potential not to donate semen during therapy and for 90 days following discontinuation of CELLCEPT [see Warnings and Precautions (5.13)].

17.12 Potential to Impair Driving and Use of Machinery

Advise patients that CELLCEPT can affect the ability to drive or operate machines. Patients should avoid driving or operating machines if they experience somnolence, confusion, dizziness, tremor or hypotension during treatment with CELLCEPT [see Warnings and Precautions (5.15)].

Distributed by:

Genentech USA, Inc.
A Member of the Roche Group
1 DNA Way
South San Francisco, CA 94080-4990

MEDICATION GUIDE

CELLCEPT® [SEL-sept]
(mycophenolate mofetil capsules)
(mycophenolate mofetil tablets)

CELLCEPT® [SEL-sept]
(mycophenolate mofetil for oral suspension)

CELLCEPT® [SEL-sept]
(mycophenolate mofetil for injection)

Read the Medication Guide that comes with CELLCEPT before you start taking it and each time you refill your prescription. There may be new information. This Medication Guide does not take the place of talking with your doctor about your medical condition or treatment.

What is the most important information I should know about CELLCEPT?
CELLCEPT can cause serious side effects, including:
Increased risk of loss of a pregnancy (miscarriage) and higher risk of birth defects. Females who take CELLCEPT during pregnancy have a higher risk of miscarriage during the first 3 months (first trimester), and a higher risk that their baby will be born with birth defects.

- If you are a female who can become pregnant, your doctor must talk with you about acceptable birth control methods (contraceptive counseling) to use while taking CELLCEPT. You should have 1 pregnancy test immediately before starting CELLCEPT and another pregnancy test 8 to 10 days later. Pregnancy tests should be repeated during routine follow-up visits with your doctor. Talk to your doctor about the results of all of your pregnancy tests.
  You must use acceptable birth control during your entire CELLCEPT treatment and for 6 weeks after stopping CELLCEPT, unless at any time you choose to avoid sexual intercourse (abstinence) with a man completely. CELLCEPT decreases blood levels of the hormones in birth control pills that you take by mouth. Birth control pills may not work as well while you take CELLCEPT, and you could become pregnant. If you take birth control pills while using CELLCEPT you must also use another form of birth control. Talk to your doctor about other birth control methods that you can use while taking CELLCEPT.
- If you are a sexually active male whose female partner can become pregnant while you are taking CELLCEPT, use effective contraception during treatment and for at least 90 days after stopping CELLCEPT.
- If you plan to become pregnant, talk with your doctor. Your doctor will decide if other medicines to prevent rejection may be right for you.
- If you become pregnant while taking CELLCEPT, do not stop taking CELLCEPT. Call your doctor right away. You and your doctor may decide that other medicines to prevent rejection may be right for you. You and your doctor should report your pregnancy to the Mycophenolate Pregnancy Registry either:
  - By phone at 1-800-617-8191 or
  - By visiting the REMS website at: www.mycophenolateREMS.com
  The purpose of this registry is to gather information about the health of you and your baby.

Increased risk of getting certain cancers. People who take CELLCEPT have a higher risk of getting lymphoma, and other cancers, especially skin cancer. Tell your doctor if you have:

- unexplained fever, prolonged tiredness, weight loss or lymph node swelling
- a brown or black skin lesion with uneven borders, or one part of the lesion does not look like the other

- a change in the size and color of a mole
- a new skin lesion or bump
- any other changes to your health

Increased risk of getting serious infections. CELLCEPT weakens the body's immune system and affects your ability to fight infections. Serious infections can happen with CELLCEPT and can lead to hospitalizations and death. These serious infections can include:

- Viral infections. Certain viruses can live in your body and cause active infections when your immune system is weak. Viral infections that can happen with CELLCEPT include:
  - Shingles, other herpes infections, and cytomegalovirus (CMV). CMV can cause serious tissue and blood infections.
  - BK virus. BK virus can affect how your kidney works and cause your transplanted kidney to fail.
  - Hepatitis B and C viruses. Hepatitis viruses can affect how your liver works. Talk to your doctor about how hepatitis viruses may affect you.
  - COVID-19
- A brain infection called Progressive Multifocal Leukoencephalopathy (PML). In some patients, CELLCEPT may cause an infection of the brain that may cause death. You are at risk for this brain infection because you have a weakened immune system. Call your doctor right away if you have any of the following symptoms:

- weakness on one side of the body
- you do not care about things you usually care about (apathy)

- you are confused or have problems thinking
- you cannot control your muscles

- Fungal infections. Yeasts and other types of fungal infections can happen with CELLCEPT and can cause serious tissue and blood infections (See "What are the possible side effects of CELLCEPT?").

Call your doctor right away if you have any of the following signs and symptoms of infection:

- temperature of 100.5°F or greater
- cold symptoms, such as a runny nose or sore throat
- flu symptoms, such as an upset stomach, stomach pain, vomiting or diarrhea
- earache or headache

- pain during urination
- white patches in the mouth or throat
- unexpected bruising or bleeding
- cuts, scrapes or incisions that are red, warm and oozing pus

See "What are the possible side effects of CELLCEPT?" for information about other serious side effects.

What is CELLCEPT?

- CELLCEPT is a prescription medicine to prevent rejection (antirejection medicine) in people who have received a kidney, heart or liver transplant. Rejection is when the body's immune system perceives the new organ as a "foreign" threat and attacks it.
- CELLCEPT is used with other medicines containing cyclosporine and corticosteroids.

Who should not take CELLCEPT?
Do not take CELLCEPT if you have a history of allergic reactions to mycophenolate mofetil or any of the ingredients in CELLCEPT. See the end of this Medication Guide for a complete list of ingredients in CELLCEPT.

What should I tell my doctor before taking CELLCEPT?
Tell your doctor about all of your medical conditions, including if you:

- have any digestive problems, such as ulcers.
- have Phenylketonuria (PKU). CELLCEPT oral suspension contains aspartame (a source of phenylalanine).
- have Lesch-Nyhan syndrome, Kelley-Seegmiller syndrome, or another rare inherited deficiency hypoxanthine-guanine phosphoribosyl-transferase (HGPRT). You should not take CELLCEPT if you have one of these disorders.
- plan to receive any vaccines. People taking CELLCEPT should not receive live vaccines. Some vaccines may not work as well during treatment with CELLCEPT.
- are pregnant or plan to become pregnant. See "What is the most important information I should know about CELLCEPT?"
- are breastfeeding or plan to breastfeed. It is not known if CELLCEPT passes into breast milk. You and your doctor will decide if you will take CELLCEPT or breastfeed.

Tell your healthcare provider about all the medicines you take, including prescription and over-the-counter medicines, vitamins and herbal supplements. Some medicines may affect the way CELLCEPT works, and CELLCEPT may affect how some medicines work.
Especially tell your doctor if you take:

- birth control pills (oral contraceptives). See "What is the most important information I should know about CELLCEPT?"
- sevelamer (Renagel®, Renvela™). These products should be taken at least 2 hours after taking CELLCEPT.
- acyclovir (Zovirax®), valacyclovir (Valtrex®), ganciclovir (CYTOVENE®-IV, Vitrasert®), valganciclovir (VALCYTE®).
- rifampin (Rifater®, Rifamate®, Rimactane®, Rifadin®).
- antacids that contain magnesium and aluminum (CELLCEPT and the antacid should not be taken at the same time).
- proton pump inhibitors (PPIs) (Prevacid®, Protonix®).
- sulfamethoxazole/trimethoprim (BACTRIM™, BACTRIM DS™).
- norfloxacin (Noroxin®) and metronidazole (Flagyl®, Flagyl® ER, Flagyl® IV, Metro IV, Helidac®, Pylera™).
- ciprofloxacin (Cipro®, Cipro® XR, Ciloxan®, Proquin® XR) and amoxicillin plus clavulanic acid (Augmentin®, Augmentin XR™).
- azathioprine (Azasan®, Imuran®).
- cholestyramine (Questran Light®, Questran®, Locholest Light, Locholest, Prevalite®).

Know the medicines you take. Keep a list of them to show to your doctor or nurse and pharmacist when you get a new medicine. Do not take any new medicine without talking with your doctor.

How should I take CELLCEPT?

- Take CELLCEPT exactly as prescribed.
- Do not stop taking CELLCEPT or change the dose unless your doctor tells you to.
- If you miss a dose of CELLCEPT, or you are not sure when you took your last dose, take your prescribed dose of CELLCEPT as soon as you remember. If your next dose is less than 2 hours away, skip the missed dose and take your next dose at your normal scheduled time. Do not take 2 doses at the same time. Call your doctor if you are not sure what to do.
- Take CELLCEPT capsules, tablets and oral suspension on an empty stomach, unless your doctor tells you otherwise. Do not crush CELLCEPT tablets.
- Do not open or crush CELLCEPT capsules.
- If you are not able to swallow CELLCEPT tablets or capsules, your doctor may prescribe CELLCEPT Oral Suspension. This is a liquid form of CELLCEPT. Your pharmacist will mix the medicine before you pick it up from a pharmacy.
- Do not mix CELLCEPT Oral Suspension with any other medicine. CELLCEPT Oral Suspension should not be mixed with any type of liquids before taking the dose. See the Instructions for Use at the end of this Medication Guide for detailed instructions about how to take CELLCEPT Oral Suspension the right way.
- Do not breathe in (inhale) or let CELLCEPT powder or oral suspension come in contact with your skin or mucous membranes.
  - If you accidentally get the powder or oral suspension on the skin, wash the area well with soap and water.
  - If you accidentally get the powder or oral suspension in your eyes or other mucous membranes, flush with plain water.
- If you take too much CELLCEPT, call your doctor or the poison control center right away.

What should I avoid while taking CELLCEPT?

- Avoid becoming pregnant. (See "What is the most important information I should know about CELLCEPT?").
- Limit the amount of time you spend in sunlight. Avoid using tanning beds or sunlamps. People who take CELLCEPT have a higher risk of getting skin cancer (See "What is the most important information I should know about CELLCEPT?"). Wear protective clothing when you are in the sun and use a broad-spectrum sunscreen with a high protection factor. This is especially important if your skin is very fair or if you have a family history of skin cancer.
- You should not donate blood while taking CELLCEPT and for at least 6 weeks after stopping CELLCEPT.
- You should not donate sperm while taking CELLCEPT and for 90 days after stopping CELLCEPT.
- CELLCEPT may influence your ability to drive and use machines (See "What are the possible side effects of CELLCEPT?". If you experience drowsiness, confusion, dizziness, tremor, or low blood pressure during treatment with CELLCEPT, you should be cautious about driving or using heavy machines.

What are the possible side effects of CELLCEPT?
CELLCEPT may cause serious side effects, including:

- See "What is the most important information I should know about CELLCEPT?"
- Low blood cell counts. People taking high doses of CELLCEPT each day may have a decrease in blood counts, including:
  - white blood cells, especially neutrophils. Neutrophils fight against bacterial infections. You have a higher chance of getting an infection when your white blood cell count is low. This is most common from 1 month to 6 months after your transplant.
  - red blood cells. Red blood cells carry oxygen to your body tissues. You have a higher chance of getting severe anemia when your red blood cell count is low.
  - platelets. Platelets help with blood clotting.
  Your doctor will do blood tests before you start taking CELLCEPT and during treatment with CELLCEPT to check your blood cell counts. Tell your doctor right away if you have any signs of infection (See "What is the most important information I should know about CELLCEPT?"), including any unexpected bruising or bleeding. Also, tell your doctor if you have unusual tiredness, lack of energy, dizziness or fainting.
- Stomach problems. Stomach problems including intestinal bleeding, a tear in your intestinal wall (perforation) or stomach ulcers can happen in people who take CELLCEPT. Bleeding can be severe and you may have to be hospitalized for treatment. Call your doctor right away if you have sudden or severe stomach-area pain or stomach-area pain that does not go away, or if you have diarrhea.
- Inflammatory reactions. Some people taking CELLCEPT may have an inflammatory reaction with fever, joint stiffness, joint pain, and muscle pain. Some of these reactions may require hospitalization. This reaction could happen within weeks to months after your treatment with CELLCEPT starts or if your dose is increased. Call your doctor right away if you experience these symptoms.
- Allergic (hypersensitivity) reactions. Allergic reactions, including a severe allergic reaction called anaphylaxis, can happen after taking CELLCEPT. Stop taking CELLCEPT and get emergency medical help right away if you have any of the following symptoms of an allergic reaction:

- swelling of the face, lips, tongue, or throat
- rash, hives, or itching
- fainting, dizziness, feeling lightheaded

- trouble breathing or swallowing
- fast heartbeat
- chest pain

The most common side effects of CELLCEPT include:

- diarrhea
- blood problems including low white and red blood cell counts
- infections
- blood pressure problems
- fast heartbeat
- swelling of the lower legs, ankles and feet

- changes in laboratory blood levels, including high levels of blood sugar (hyperglycemia)
- stomach problems including diarrhea, constipation, nausea and vomiting
- rash
- nervous system problems such as headache, dizziness and tremor

Side effects that can happen more often in children than in adults taking CELLCEPT include:

- stomach area pain
- fever
- infection
- pain
- blood infection (sepsis)
- diarrhea

- vomiting
- sore throat
- colds (respiratory tract infections)
- high blood pressure
- low white blood cell count
- low red blood cell count

These are not all of the possible side effects of CELLCEPT. Tell your doctor about any side effect that bothers you or that does not go away.
Call your doctor for medical advice about side effects. You may report side effects to FDA at 1-800-FDA-1088.
You may also report side effects to Genentech at 1-888-835-2555.

How should I store CELLCEPT?

- Store CELLCEPT capsules and tablets at room temperature between 59°F to 86°F (15°C to 30°C).
- Keep CELLCEPT tablets in the light resistant container that it comes in.
- Store CELLCEPT Oral Suspension at room temperature between 59°F to 86°F (15°C to 30°C), for up to 60 days. You can also store CELLCEPT Oral Suspension in the refrigerator between 36°F to 46°F (2°C to 8°C). Do not freeze.

Keep CELLCEPT and all medicines out of the reach of children.

General information about the safe and effective use of CELLCEPT.
Medicines are sometimes prescribed for purposes other than those listed in a Medication Guide. Do not use CELLCEPT for a condition for which it was not prescribed. Do not give CELLCEPT to other people, even if they have the same symptoms that you have. It may harm them.
This Medication Guide summarizes the most important information about CELLCEPT. If you would like more information, talk with your doctor. You can ask your doctor or pharmacist about CELLCEPT that is written for health professionals.

What are the ingredients in CELLCEPT?
Active ingredient: mycophenolate mofetil
Inactive ingredients:
CELLCEPT 250 mg capsules: croscarmellose sodium, magnesium stearate, povidone (K-90) and pregelatinized starch. The capsule shells contain black iron oxide, FD&C blue #2, gelatin, red iron oxide, silicon dioxide, sodium lauryl sulfate, titanium dioxide, and yellow iron oxide.
CELLCEPT 500 mg tablets: croscarmellose sodium, FD&C blue #2 aluminum lake, hydroxypropyl cellulose, hydroxypropyl methylcellulose, magnesium stearate, microcrystalline cellulose, polyethylene glycol 400, povidone (K-90), red iron oxide, and titanium dioxide.
CELLCEPT Oral Suspension: aspartame, citric acid anhydrous, colloidal silicon dioxide, methylparaben, mixed fruit flavor, sodium citrate dihydrate, sorbitol, soybean lecithin, and xanthan gum.
CELLCEPT Intravenous: polysorbate 80, and citric acid. Sodium hydroxide and hydrochloric acid may have been used in the manufacture of CELLCEPT Intravenous to adjust the pH.
Distributed by:
Genentech USA, Inc.
A Member of the Roche Group
1 DNA Way
South San Francisco, CA 94080-4990
CELLCEPT and VALCYTE are registered trademarks of Hoffmann-La Roche Inc.
© 2025 Genentech, Inc. All rights reserved.
For more information, call 1-888-835-2555 or visit www.gene.com/gene/products/information/CELLCEPT.

This Medication Guide has been approved by the U.S. Food and Drug Administration.

Revised: May 2025

Instructions for Use CELLCEPT® [SEL-sept] (mycophenolate mofetil) oral suspension

Read this Instructions for Use before you take or give CELLCEPT for the first time and each time you get a refill. There may be new information. This information does not take the place of talking to your healthcare provider about your medical condition or treatment.

Important:

- Always use the oral dispenser provided with CELLCEPT Oral Suspension to make sure you measure the right amount of medicine. If your CELLCEPT Oral Suspension does not come with the oral dispenser, contact your pharmacist.
- Call your pharmacist if your oral dispenser is lost or damaged.
- Your pharmacist will write the expiration date on your CELLCEPT Oral Suspension bottle label. Do not use CELLCEPT after the expiration date.
- Ask your doctor or pharmacist if you have any questions or are unsure about how to take or give the right amount of medicine.
- The CELLCEPT Oral Suspension should not be mixed with any type of liquids before taking or giving the dose.
- Do not let the CELLCEPT Oral Suspension come in contact with the skin. If this happens, wash the skin well with soap and water. If the CELLCEPT Oral Suspension gets in the eyes, rinse the eyes with plain water.
- If you spill any CELLCEPT Oral Suspension, wipe it up using paper towels wet with water. Put the child-resistant bottle cap back on the bottle and wipe the outside of the bottle with wet paper towels.

Supplies needed to take or give a dose of CELLCEPT Oral Suspension:

To take or give a dose of CELLCEPT Oral Suspension, you will need the bottle of medicine and the oral dispenser provided with the medicine (See Figure 1). Your pharmacist will insert the bottle adapter in the CELLCEPT Oral Suspension bottle. Do not remove the bottle adapter from the bottle.

Figure 1

Taking or giving a dose of CELLCEPT Oral Suspension:

Step 1: | With the child-resistant cap on the bottle, shake the bottle well for about 5 seconds before each use.
Step 2: | Open the bottle by firmly pressing down on the child-resistant bottle cap and turning it to the left (counter-clockwise). Do not throw away the child-resistant bottle cap.
Step 3: | Place the bottle on a flat surface. Before inserting the tip of the oral dispenser into the bottle adapter, push the plunger completely down toward the tip of the oral dispenser. Use 1 hand to hold the bottle upright. Insert the oral dispenser tip firmly into the opening of the bottle adapter.
Step 4: | Carefully turn the bottle upside down with the oral dispenser tip in place. Slowly pull the plunger down to withdraw your prescribed dose. Do not pull the plunger out of the oral dispenser (See Figure 2).
Step 5: | Leave the oral dispenser tip in the bottle and turn the bottle to an upright position. Slowly remove the oral dispenser tip from the bottle. If there are air bubbles in the oral dispenser or if you have withdrawn the wrong dose, insert the oral dispenser tip back into the bottle adapter while the bottle is in an upright position. Push the plunger gently all the way up so the CELLCEPT Oral Suspension flows back into the bottle. Repeat Step 4.
Step 6: | Place the tip of the oral dispenser in the mouth directed towards the cheek and slowly push the plunger down until the oral dispenser is empty.
Step 7: | Put the child-resistant bottle cap back on the bottle and turn the cap to the right (clockwise) to close the bottle. Keep the bottle tightly closed after each use.
Step 8: | Rinse the oral dispenser under running tap water after each use:; - Remove the plunger from the oral dispenser. - Rinse the oral dispenser and plunger with water only and let them air dry on a paper towel. - When the oral dispenser and plunger are dry, put the plunger back in the oral dispenser for the next use. Do not throw away the oral dispenser. Store the oral dispenser in a clean, dry place. - Do not boil the oral dispenser. Do not use solvent-containing wipes to clean the oral dispenser. Do not use cloths or wipes to dry the oral dispenser.

How should I store CELLCEPT Oral Suspension?

- Store the CELLCEPT Oral Suspension at room temperature between 59°F to 86°F (15°C to 30°C), for up to 60 days. You can also store the CELLCEPT Oral Suspension in the refrigerator between 36°F to 46°F (2°C to 8°C).)
- Do not freeze.

Keep CELLCEPT Oral Suspension and all medicines out of the reach of children.

Distributed by:
Genentech USA, Inc.
A Member of the Roche Group
1 DNA Way
South San Francisco, CA 94080-4990
©2022 Genentech, Inc. All rights reserved.

This Instructions for Use has been approved by the U.S. Food and Drug Administration.

Revised: August 2022

Representative sample of labeling (see the HOW SUPPLIED section for complete listing):

PRINCIPAL DISPLAY PANEL - 500 mg Tablet Bottle Carton

NDC 0004-0260-43

CellCept®
(mycophenolate
mofetil tablets)

500 mg

Each tablet contains
500 mg mycophenolate mofetil.

Rx only

Attention Pharmacist: Dispense the
accompanying Medication Guide to each
patient. For additional Medication Guides call
1-800-617-8191 or visit www.gene.com/gene/
products/information/cellcept.

500 tablets

Genentech

10235320

PRINCIPAL DISPLAY PANEL - 250 mg Capsule Bottle Carton

NDC 0004-0259-43

CellCept®
(mycophenolate
mofetil capsules)

250 mg

Each capsule contains
250 mg mycophenolate mofetil.

Rx only

Attention Pharmacist: Dispense the
accompanying Medication Guide to each
patient. For additional Medication Guides call
1-800-617-8191 or visit www.gene.com/gene/
products/information/cellcept.

500 capsules

Genentech

10235316

PRINCIPAL DISPLAY PANEL - 500 mg Vial Carton

NDC 0004-0298-09

CellCept® Intravenous
(mycophenolate mofetil for injection)

500 mg

FOR INTRAVENOUS INFUSION ONLY.

Each single-dose vial contains the equivalent of 500 mg mycophenolate mofetil (equivalent to 542 mg of
mycophenolate mofetil hydrochloride), 25 mg polysorbate 80 and 5 mg citric acid. Sodium hydroxide or
hydrochloric acid may have been used to adjust pH.

Attention Pharmacist: Dispense the accompanying Medication Guide to each patient. For additional
Medication Guides, call 1-800-617-8191 or visit www.gene.com/gene/products/information/cellcept.

Rx only
4 Single-Dose Vials

Genentech

10215811

PRINCIPAL DISPLAY PANEL - 200 mg/mL Bottle Carton

NDC 0004-0261-29

CellCept®
Oral Suspension
(mycophenolate
mofetil for oral
suspension)

200 mg/mL

Each mL contains 200 mg mycophenolate
mofetil after constitution.

Attention Pharmacist: Dispense the accompanying
Medication Guide to each patient. For additional
Medication Guides, call 1-800-617-8191 or visit
www.gene.com/gene/products/information/cellcept.

Rx only

Genentech

10225425